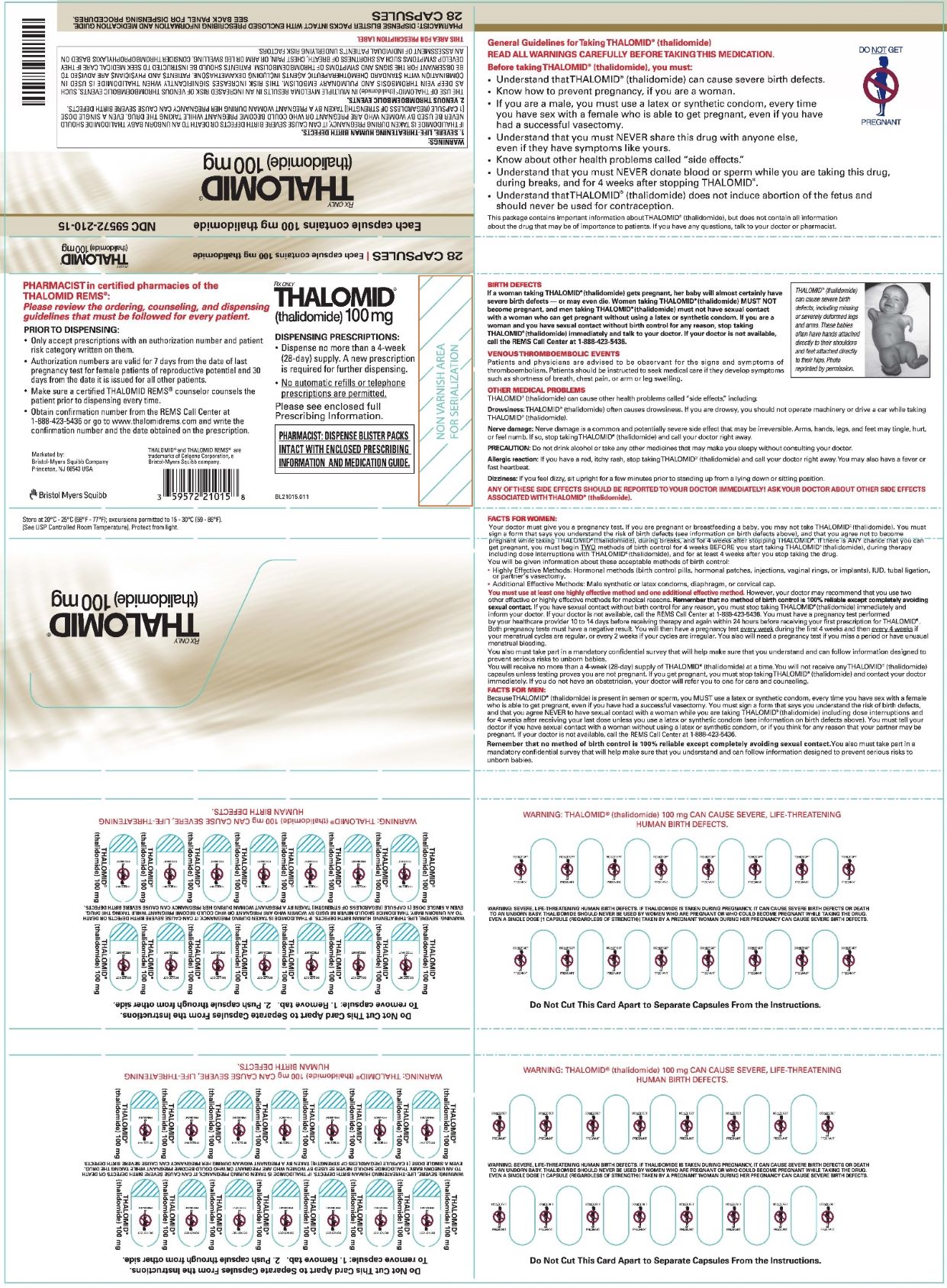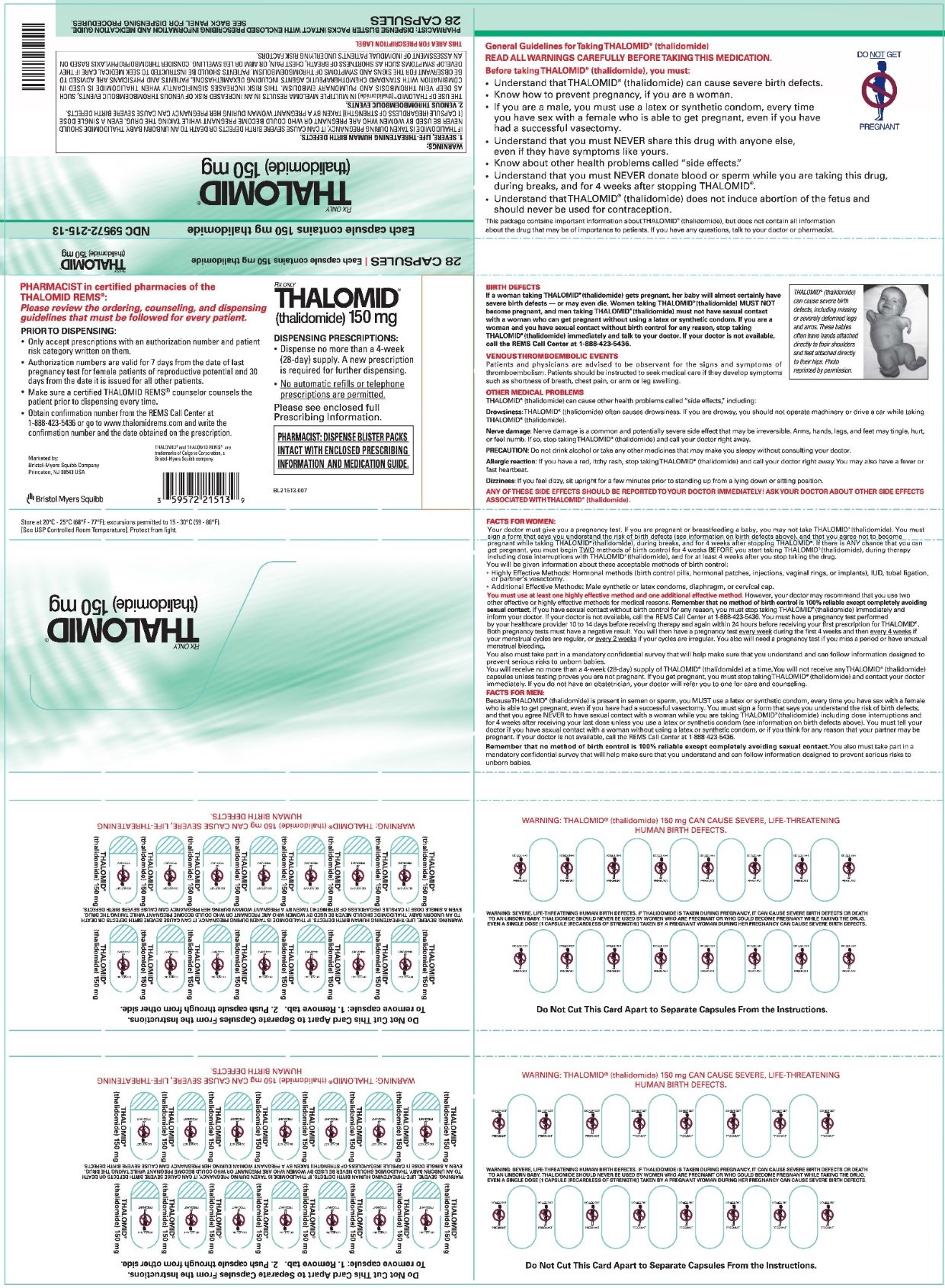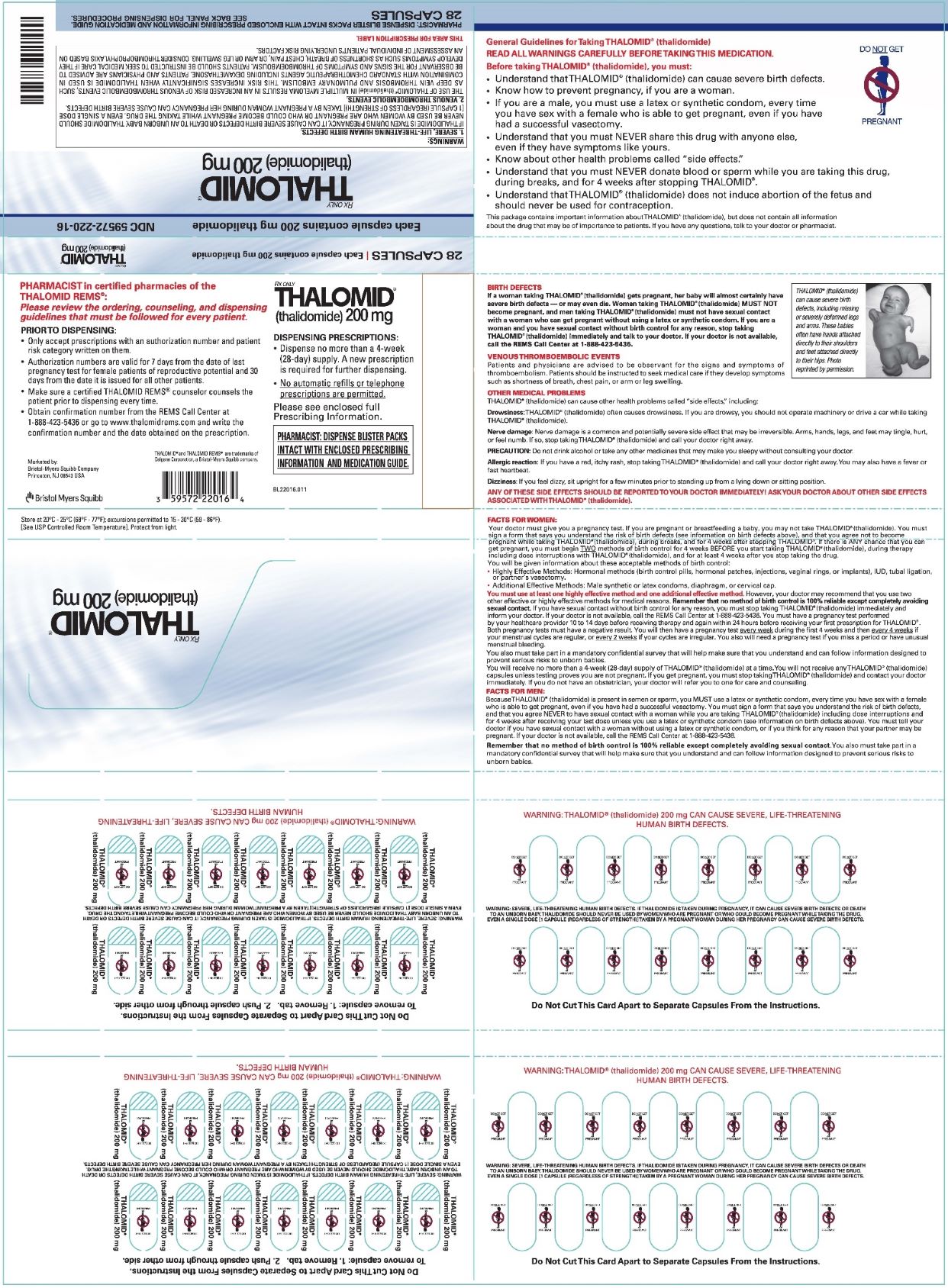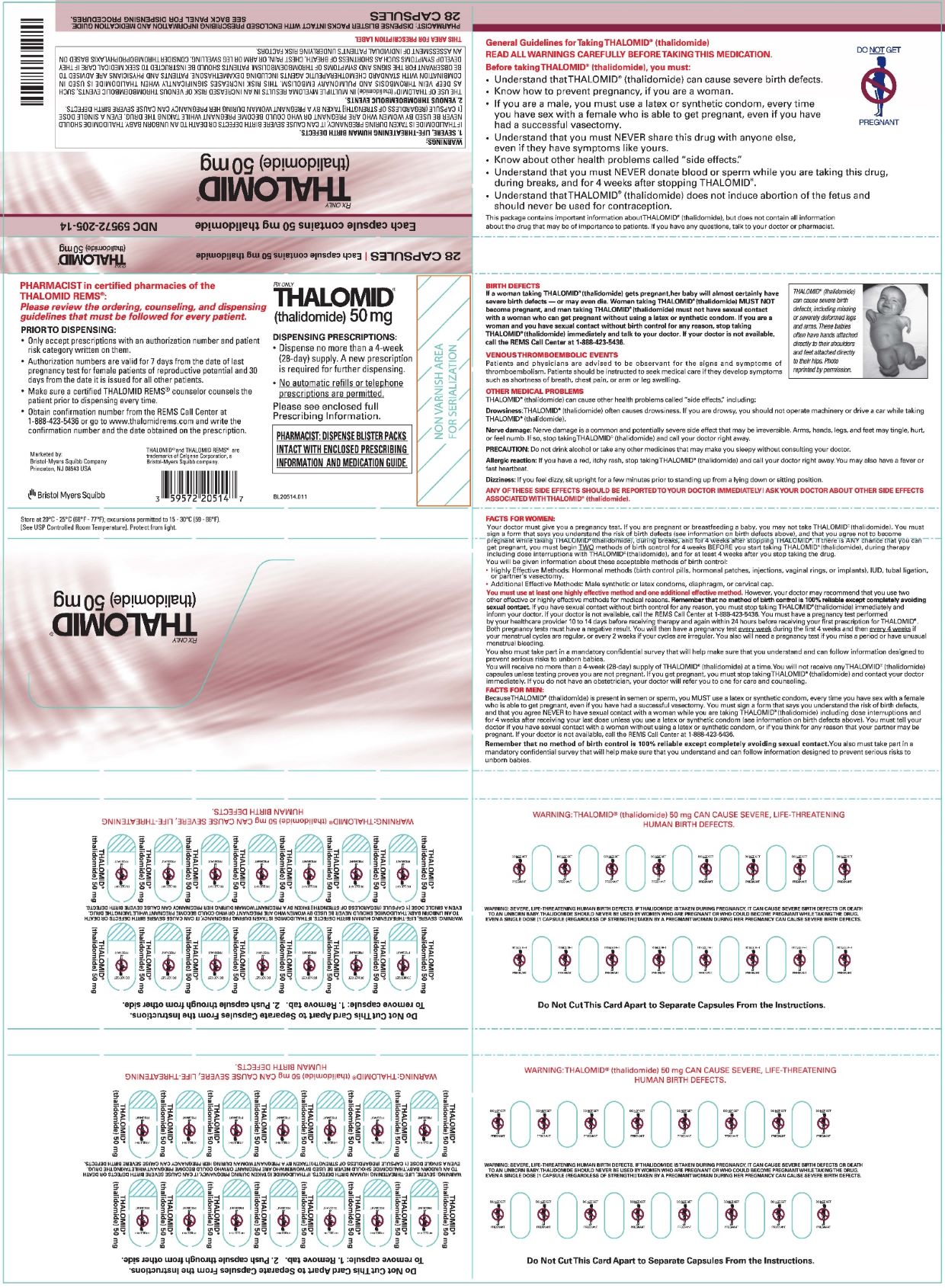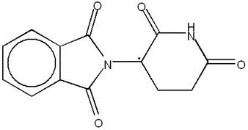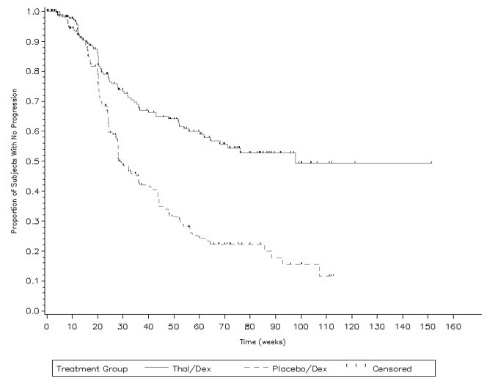 DRUG LABEL: Thalomid
NDC: 59572-205 | Form: CAPSULE
Manufacturer: Celgene Corporation
Category: prescription | Type: HUMAN PRESCRIPTION DRUG LABEL
Date: 20230324

ACTIVE INGREDIENTS: THALIDOMIDE 50 mg/1 1
INACTIVE INGREDIENTS: STARCH, CORN; MAGNESIUM STEARATE

HIGHLIGHTS OF PRESCRIBING INFORMATION

These highlights do not include all the information needed to use THALOMID® safely and effectively. See full prescribing information for THALOMID.
THALOMID (thalidomide) capsules, for oral use
Initial U.S. Approval: 1998

WARNING: EMBRYO-FETAL TOXICITY AND VENOUS THROMBOEMBOLISM

See full prescribing information for complete boxed warning.

EMBRYO -FETAL TOXICITY

- If THALOMID is taken during pregnancy, it can cause severe birth defects or embryo-fetal death. THALOMID should never be used by females who are pregnant or who could be pregnant while taking the drug. Even a single dose [1 capsule (regardless of strength)] taken by a pregnant woman during her pregnancy can cause severe birth defects.
- Pregnancy must be excluded before start of treatment. Prevent pregnancy thereafter by the use of two reliable methods of contraception. (5.1, 8.3)

THALOMID is only available through a restricted distribution program, the THALOMID REMS® program (5.2).

VENOUS THROMBOEMBOLISM

- Significant increased risk of deep vein thrombosis (DVT) and pulmonary embolism (PE) in patients with multiple myeloma receiving THALOMID with dexamethasone (5.3).

1 INDICATIONS AND USAGE

- THALOMID in combination with dexamethasone is indicated for the treatment of patients with newly diagnosed multiple myeloma (MM). (1.1)
- THALOMID is indicated for the acute treatment of the cutaneous manifestations of moderate to severe erythema nodosum leprosum (ENL).
  THALOMID is not indicated as monotherapy for such ENL treatment in the presence of moderate to severe neuritis.
  THALOMID is also indicated as maintenance therapy for prevention and suppression of the cutaneous manifestations of ENL recurrence. (1.2)

2 DOSAGE AND ADMINISTRATION

- MM: 200 mg orally once daily. The recommended dose of dexamethasone is 40 mg/day on days 1-4, 9-12, and 17-20 every 28 days. (2.2)
- ENL: 100 to 300 mg/day for an episode of cutaneous ENL.
  Up to 400 mg/day for severe cutaneous ENL. (2.3)

3 DOSAGE FORMS AND STRENGTHS

Capsules: 50 mg, 100 mg, 150 mg and 200 mg. (3)

4 CONTRAINDICATIONS

- Pregnancy (Boxed Warning, 4.1, 5.1, 5.2, 8.1, 17)
- Demonstrated hypersensitivity to the drug or its components (4.2, 5.16, 6.2)

5 WARNINGS AND PRECAUTIONS

- Ischemic heart disease (including myocardial infarction) and stroke have been observed in patients treated with THALOMID in combination with dexamethasone. (5.3)
- Increased Mortality: Observed in patients with MM when pembrolizumab was added to dexamethasone and a thalidomide analogue. (5.4)
- Drowsiness and Somnolence: Instruct patients to avoid situations where drowsiness may be a problem and not to take other medications that may cause drowsiness. (5.5)
- Peripheral Neuropathy: Monitor patients for signs or symptoms of peripheral neuropathy during treatment. Discontinue THALOMID if symptoms of drug-induced peripheral neuropathy occur, if clinically appropriate. (5.6)
- Dizziness and Orthostatic Hypotension: Advise patients to sit upright for a few minutes prior to standing up from a recumbent position. (5.7)
- Neutropenia and Thrombocytopenia: Patients may require dose interruption and/or dose reduction. (5.8, 5.9)
- Increased HIV Viral Load: Measure viral load during treatment. (5.10)
- Bradycardia: Monitor patients for bradycardia and possible syncope. Dose reduction or discontinuation may be required. (5.11)
- Severe Cutaneous Reactions: Discontinue THALOMID for severe reactions. (5.12)
- Seizures: Monitor patients with a history of seizures or other risk factors for acute seizure activity. (5.13)
- Tumor Lysis Syndrome: Monitor patients at risk (e.g., those with high tumor burden prior to treatment) and take appropriate precautions. (5.14)
- Hypersensitivity: Monitor patients for potential hypersensitivity. Discontinue THALOMID for angioedema and anaphylaxis. (5.16)

6 ADVERSE REACTIONS

- MM: The most common adverse reactions (≥ 20%) are fatigue, hypocalcemia, edema, constipation, neuropathy-sensory, dyspnea, muscle weakness, leukopenia, neutropenia, rash/desquamation, confusion, anorexia, nausea, anxiety/agitation, asthenia, tremor, fever, weight loss, thrombosis/embolism, neuropathy-motor, weight gain, dizziness, and dry skin. (6.1)
- ENL: The most common adverse reactions (≥ 10%) are somnolence, rash, and headache. (6.1)

To report SUSPECTED ADVERSE REACTIONS or embryo-fetal exposure: contact Bristol Myers Squibb at 1-800-721-5072 or 1-888-423-5436, respectively, or FDA at 1-800-FDA-1088 or www.fda.gov/medwatch.

7 DRUG INTERACTIONS

- Use caution if other drugs which have sedative and hypnotic properties, slow cardiac conduction and/or cause peripheral neuropathy must be used. (7.1, 7.2, 7.3)
- It is not known whether concomitant use of hormonal contraceptives further increases the risk of thromboembolism with THALOMID. (5.15, 7.4)
- Patients taking concomitant therapies such as erythropoietin stimulating agents or estrogen containing therapies may have an increased risk of thromboembolism. (7.7)

8 USE IN SPECIFIC POPULATIONS

- Lactation: Advise women not to breastfeed. (8.2)

FULL PRESCRIBING INFORMATION

WARNING: EMBRYO-FETAL TOXICITY AND VENOUS THROMBOEMBOLISM

EMBRYO-FETAL TOXICITY

If THALOMID is taken during pregnancy, it can cause severe birth defects or embryo-fetal death. THALOMID should never be used by females who are pregnant or who could become pregnant while taking the drug. Even a single dose [1 capsule (regardless of strength)] taken by a pregnant woman during her pregnancy can cause severe birth defects.

Because of this toxicity and in an effort to make the chance of embryo-fetal exposure to THALOMID as negligible as possible, THALOMID is approved for marketing only through a special restricted distribution program: THALOMID REMS program, approved by the Food and Drug Administration.

Information about THALOMID and the THALOMID REMS program is available at www.thalomidrems.com or by calling the REMS Call Center at 1-888-423-5436.

VENOUS THROMBOEMBOLISM

The use of THALOMID in multiple myeloma results in an increased risk of venous thromboembolism, such as deep venous thrombosis and pulmonary embolism. This risk increases significantly when THALOMID is used in combination with standard chemotherapeutic agents including dexamethasone. In one controlled trial, the rate of venous thromboembolism was 22.5% in patients receiving THALOMID in combination with dexamethasone compared to 4.9% in patients receiving dexamethasone alone (p = 0.002). Patients and physicians are advised to be observant for the signs and symptoms of thromboembolism. Instruct patients to seek medical care if they develop symptoms such as shortness of breath, chest pain, or arm or leg swelling. Consider thromboprophylaxis based on an assessment of individual patients' underlying risk factors.

1 INDICATIONS AND USAGE

1.1 Multiple Myeloma

THALOMID in combination with dexamethasone is indicated for the treatment of patients with newly diagnosed multiple myeloma (MM) [see Clinical Studies (14.1)].

1.2 Erythema Nodosum Leprosum

THALOMID is indicated for the acute treatment of the cutaneous manifestations of moderate to severe erythema nodosum leprosum (ENL).

THALOMID is not indicated as monotherapy for such ENL treatment in the presence of moderate to severe neuritis.

THALOMID is also indicated as maintenance therapy for prevention and suppression of the cutaneous manifestations of ENL recurrence [see Clinical Studies (14.2)].

2 DOSAGE AND ADMINISTRATION

2.1 Required Baseline Testing

Drug prescribing to females of reproductive potential is contingent upon initial and continued negative results of pregnancy testing [see Warnings and Precautions (5.1 and 5.2)].

THALOMID must only be administered in compliance with all of the terms outlined in the THALOMID REMS program. THALOMID may only be prescribed by prescribers certified with the THALOMID REMS program and may only be dispensed by pharmacists certified with the THALOMID REMS program.

2.2 Recommended Dosage for Multiple Myeloma

The recommended dose of THALOMID in combination with dexamethasone is 200 mg once daily (in 28-day treatment cycles) orally with water, preferably at bedtime and at least 1 hour after the evening meal. The dose of dexamethasone is 40 mg daily administered orally on days 1-4, 9-12, and 17-20 every 28 days.

2.3 Recommended Dosage for Erythema Nodosum Leprosum

The recommended dose of THALOMID for an episode of cutaneous ENL is 100 to 300 mg/day once daily orally with water, preferably at bedtime and at least 1 hour after the evening meal. Initiate dosing for patients weighing less than 50 kilograms at the low end of the dose range.

Consider dosing in the higher dosage range for patients with a severe cutaneous ENL reaction, or in those who have previously required higher doses to control the reaction (possibly up to 400 mg/day) once daily at bedtime or in divided doses with water, at least 1 hour after meals.

Consider concomitant use of corticosteroids in patients with moderate to severe neuritis associated with a severe ENL reaction. Steroid usage can be tapered and discontinued when the neuritis has ameliorated.

Continue dosing with THALOMID until signs and symptoms of active reaction have subsided, usually a period of at least 2 weeks. Patients may then be tapered off medication in 50 mg decrements every 2 to 4 weeks.

Patients who have a documented history of requiring prolonged maintenance treatment to prevent the recurrence of cutaneous ENL or who flare during tapering should be maintained on the minimum dose necessary to control the reaction. Tapering off medication should be attempted every 3 to 6 months, in decrements of 50 mg every 2 to 4 weeks.

2.4 Dosage Modifications for Adverse Reactions

Interrupt THALOMID for constipation, somnolence, or peripheral neuropathy. Consider a reduced dose upon resumption of treatment.

Consider dose reduction, delay, or discontinuation in patients who develop National Cancer Institute Common Toxicity Criteria (NCI CTC) Grade 3 or 4 adverse reactions and/or based on clinical judgment.

Permanently discontinue THALOMID for angioedema, anaphylaxis, Grade 4 rash, skin exfoliation, bullae, or any other severe dermatologic reactions [see Warnings and Precautions (5.12 and 5.16)].

3 DOSAGE FORMS AND STRENGTHS

Capsules:

- 50 mg white, printed with "BMS/50 mg" on the body and a "Do Not Get Pregnant" logo on the cap.
- 100 mg tan, printed with "BMS/100 mg" on the body and a "Do Not Get Pregnant" logo on the cap.
- 150 mg tan body printed with "BMS/150 mg" and blue cap printed with a "Do Not Get Pregnant" logo.
- 200 mg blue, printed with "BMS/200 mg" on the body and a "Do not Get Pregnant" logo on the cap.

4 CONTRAINDICATIONS

4.1 Pregnancy

THALOMID is contraindicated in females who are pregnant. THALOMID can cause fetal harm when administered to a pregnant female [see Boxed Warning, Warnings and Precautions (5.1) and Use in Specific Populations (8.1)]. THALOMID is a powerful human teratogen, inducing a high frequency of severe and life-threatening birth defects, even after a single dose [see Boxed Warning]. Mortality at or shortly after birth has been reported in about 40% of infants. If this drug is used during pregnancy, or if the patient becomes pregnant while taking this drug, the patient should be apprised of the potential risk to a fetus. If pregnancy occurs during THALOMID treatment, the drug should be discontinued immediately.

4.2 Hypersensitivity

THALOMID is contraindicated in patients who have demonstrated hypersensitivity to the drug or its components [see Warnings and Precautions (5.16)].

5 WARNINGS AND PRECAUTIONS

5.1 Embryo-Fetal Toxicity

THALOMID is a powerful human teratogen that induces a high frequency of severe and life-threatening birth defects, even after a single dose. Mortality at or shortly after birth has been reported in about 40% of infants. When there is no satisfactory alternative treatment, females of reproductive potential may be treated with THALOMID provided adequate precautions are taken to avoid pregnancy. THALOMID is only available through the THALOMID REMS program [see Warnings and Precautions (5.2)].

Oral ingestion is the only type of maternal THALOMID exposure known to result in drug-associated birth defects. There are no specific data available regarding the reproductive risks of cutaneous absorption or inhalation of THALOMID; however, females of reproductive potential should avoid contact with THALOMID Capsules. THALOMID Capsules should be stored in blister packs until ingestion. If there is contact with non-intact THALOMID capsules or the powder contents, the exposed area should be washed with soap and water.

If healthcare providers or other care givers are exposed to body fluids from patients receiving THALOMID, the exposed area should be washed with soap and water. Appropriate precautions should be utilized, such as wearing gloves to prevent the potential cutaneous exposure to THALOMID.

Females of Reproductive Potential

Females of reproductive potential must avoid pregnancy for at least 4 weeks before beginning THALOMID therapy, during therapy, during dose interruptions and for at least 4 weeks after completing therapy.

Females must commit either to abstain continuously from heterosexual sexual intercourse or to use two methods of reliable birth control, beginning 4 weeks prior to initiating treatment with THALOMID, during therapy, during dose interruptions and continuing for 4 weeks following discontinuation of THALOMID therapy.

Two negative pregnancy tests must be obtained prior to initiating therapy. The first test should be performed within 10-14 days and the second test within 24 hours prior to prescribing THALOMID therapy and then weekly during the first month, then monthly thereafter in females with regular menstrual cycles or every 2 weeks in females with irregular menstrual cycles [see Use in Specific Populations (8.3)].

Males

Thalidomide is present in the semen of patients receiving THALOMID. Therefore, males must always use a latex or synthetic condom during any sexual contact with females of reproductive potential while taking THALOMID and for up to 4 weeks after discontinuing THALOMID, even if they have undergone a successful vasectomy. Male patients taking THALOMID must not donate sperm [see Use in Specific Populations (8.3)].

Blood Donation

Patients must not donate blood during treatment with THALOMID and for 4 weeks following discontinuation of the drug because the blood might be given to a pregnant female patient whose fetus must not be exposed to THALOMID.

5.2 THALOMID REMS Program

Because of the embryo-fetal risk [see Warnings and Precautions (5.1)], THALOMID is available only through a restricted program under a Risk Evaluation and Mitigation Strategy (REMS), the THALOMID REMS program.

Required components of the THALOMID REMS program include the following:

- Prescribers must be certified with the THALOMID REMS program by enrolling and complying with the REMS requirements.
- Patients must sign a Patient-Physician Agreement Form and comply with the REMS requirements. In particular, female patients of reproductive potential who are not pregnant must comply with the pregnancy testing and contraception requirements [see Use in Specific Populations (8.3)] and males must comply with contraception requirements [see Use in Specific Populations (8.3)].
- Pharmacies must be certified with the THALOMID REMS program, must only dispense to patients who are authorized to receive THALOMID and comply with REMS requirements.

Further information about the THALOMID REMS program is available at www.thalomidrems.com or by telephone at 1-888-423-5436.

5.3 Venous and Arterial Thromboembolism

The use of THALOMID in patients with MM results in an increased risk of venous thromboembolism, such as deep venous thrombosis and pulmonary embolism. This risk increases significantly when THALOMID is used in combination with standard chemotherapeutic agents including dexamethasone. In one controlled trial, the rate of venous thromboembolism was 22.5% in patients receiving THALOMID in combination with dexamethasone compared to 4.9% in patients receiving dexamethasone alone (p = 0.002).

Ischemic heart disease (11.1%), including myocardial infarction (1.3%), and stroke (cerebrovascular accident, 2.6%) have also occurred in patients with previously untreated MM treated with THALOMID and dexamethasone compared to placebo and dexamethasone (4.7%, 1.7%, and 0.9%, respectively) in one clinical trial [see Adverse Reactions (6.1)].

Consider thromboprophylaxis based on an assessment of individual patients' underlying risk factors. Patients and physicians should be observant for the signs and symptoms of thromboembolism. Advise patients to seek immediate medical care if they develop symptoms such as shortness of breath, chest pain, or arm or leg swelling [see Boxed Warning]. Agents that also may increase the risk of thromboembolism should be used with caution in patients receiving THALOMID [see Drug Interactions (7.7)].

5.4 Increased Mortality in Patients with MM When Pembrolizumab Is Added to a Thalidomide Analogue and Dexamethasone

In two randomized clinical trials in patients with MM, the addition of pembrolizumab to a thalidomide analogue plus dexamethasone, a use for which no PD-1 or PD-L1 blocking antibody is indicated, resulted in increased mortality. Treatment of patients with MM with a PD-1 or PD-L1 blocking antibody in combination with a thalidomide analogue plus dexamethasone is not recommended outside of controlled clinical trials.

5.5 Drowsiness and Somnolence

THALOMID frequently causes drowsiness and somnolence. Patients should be instructed to avoid situations where drowsiness may be a problem and not to take other medications that may cause drowsiness without adequate medical advice [see Drug Interactions (7.1)]. Advise patients as to the possible impairment of mental and/or physical abilities required for the performance of hazardous tasks, such as driving a car or operating other complex or dangerous machinery. Dose reductions may be required.

5.6 Peripheral Neuropathy

THALOMID is known to cause nerve damage that may be permanent. Peripheral neuropathy is a common (≥10%) and potentially severe adverse reaction of treatment with THALOMID that may be irreversible. Peripheral neuropathy generally occurs following chronic use over a period of months; however, peripheral neuropathy following relatively short-term use has been reported. The correlation with cumulative dose is unclear. Symptoms may occur some time after THALOMID treatment has been stopped and may resolve slowly or not at all.

Few reports of neuropathy have arisen in the treatment of ENL despite long-term THALOMID treatment. However, the inability clinically to differentiate THALOMID neuropathy from the neuropathy often seen in ENL makes it difficult to determine accurately the incidence of THALOMID-related neuropathy in patients with ENL treated with THALOMID.

Patients should be examined at monthly intervals for the first 3 months of THALOMID therapy to enable the clinician to detect early signs of neuropathy, which include numbness, tingling or pain in the hands and feet. Patients should be evaluated periodically thereafter during treatment. Patients should be regularly counseled, questioned, and evaluated for signs or symptoms of peripheral neuropathy. Consideration should be given to electrophysiological testing, consisting of measurement of sensory nerve action potential (SNAP) amplitudes at baseline and thereafter every 6 months in an effort to detect asymptomatic neuropathy. If symptoms of drug-induced neuropathy develop, THALOMID should be discontinued immediately to limit further damage, if clinically appropriate. Usually, treatment with THALOMID should only be reinitiated if the neuropathy returns to baseline status.

Medications known to be associated with neuropathy should be used with caution in patients receiving THALOMID [see Drug Interactions (7.3)].

5.7 Dizziness and Orthostatic Hypotension

Patients should also be advised that THALOMID may cause dizziness and orthostatic hypotension and that, therefore, they should sit upright for a few minutes prior to standing up from a recumbent position.

5.8 Neutropenia

Decreased white blood cell counts, including neutropenia, have been reported in association with the clinical use of THALOMID. Treatment should not be initiated with an absolute neutrophil count (ANC) of <750/mm^3. White blood cell count and differential should be monitored on an ongoing basis, especially in patients who may be more prone to neutropenia, such as patients who are HIV-seropositive. If ANC decreases to below 750/mm^3 while on treatment, the patient's medication regimen should be re-evaluated and, if the neutropenia persists, consideration should be given to withholding THALOMID if clinically appropriate.

5.9 Thrombocytopenia

Thrombocytopenia, including Grade 3 or 4 occurrences, has been reported in association with the clinical use of THALOMID. Monitor blood counts, including platelet counts. Dose reduction, delay, or discontinuation may be required. Monitor for signs and symptoms of bleeding including petechiae, epistaxis, and gastrointestinal bleeding, especially if concomitant medication may increase the risk of bleeding.

5.10 Increased HIV Viral Load

In a randomized, placebo-controlled trial of thalidomide in an HIV-seropositive patient population, plasma HIV RNA levels were found to increase (median change = 0.42 log10 copies HIV RNA/mL, p = 0.04 compared to placebo). A similar trend was observed in a second, unpublished study conducted in patients who were HIV-seropositive. The clinical significance of this increase is unknown. Both studies were conducted prior to availability of highly active antiretroviral therapy. Until the clinical significance of this finding is further understood, in HIV-seropositive patients, viral load should be measured after the first and third months of treatment and every 3 months thereafter.

5.11 Bradycardia

Bradycardia in association with THALOMID use has been reported. Cases of bradycardia have been reported, some required medical interventions. The clinical significance and underlying etiology of the bradycardia noted in some THALOMID-treated patients are presently unknown. Monitor patients for bradycardia and syncope. Dose reduction or discontinuation may be required.

Medications known to decrease heart rate should be used with caution in patients receiving THALOMID [see Drug Interactions (7.2)].

5.12 Severe Cutaneous Reactions

Severe cutaneous reactions including Stevens-Johnson syndrome (SJS), toxic epidermal necrolysis (TEN), and drug reaction with eosinophilia and systemic symptoms (DRESS) have been reported with THALOMID use. DRESS may present with a cutaneous reaction (such as rash or exfoliative dermatitis), eosinophilia, fever, and/or lymphadenopathy with systemic complications such as hepatitis, nephritis, pneumonitis, myocarditis, and/or pericarditis. These events can be fatal. THALOMID interruption or discontinuation should be considered for Grade 2-3 skin rash. Discontinue THALOMID for Grade 4 rash, exfoliative or bullous rash, or for other severe cutaneous reactions such as SJS, TEN, or DRESS, and do not resume therapy [see Dosage and Administration (2.4)].

5.13 Seizures

Although not reported from pre-marketing controlled clinical trials, seizures, including grand mal convulsions, have been reported during post-approval use of THALOMID in clinical practice. Because these events are reported voluntarily from a population of unknown size, estimates of frequency cannot be made. Most patients had disorders that may have predisposed them to seizure activity, and it is not currently known whether THALOMID has any epileptogenic influence. During therapy with THALOMID, patients with a history of seizures or with other risk factors for the development of seizures should be monitored closely for clinical changes that could precipitate acute seizure activity.

5.14 Tumor Lysis Syndrome

Monitor patients at risk of tumor lysis syndrome (e.g., patients with high tumor burden prior to treatment) and take appropriate precautions.

5.15 Contraceptive Risks

Some contraceptive methods may pose a higher risk of adverse effects or may be medically contraindicated in some patients treated with THALOMID. Because some patients may develop sudden, severe neutropenia and/or thrombocytopenia, use of an intrauterine device (IUD) or implantable contraception in these patients may carry an increased risk for infection or bleeding either at insertion, removal or during use. Treatment with THALOMID, the presence of an underlying malignancy, and/or use of an estrogen-containing contraceptive can each increase the risk of thromboembolism. It is not known if these risks of thromboembolism are additive. However, they should be taken into consideration when choosing contraceptive methods.

5.16 Hypersensitivity

Hypersensitivity, including angioedema and anaphylactic reactions to THALOMID has been reported. Signs and symptoms have included the occurrence of erythematous macular rash, possibly associated with fever, tachycardia, and hypotension, and if severe, may necessitate interruption of therapy. If the reaction recurs when dosing is resumed, THALOMID should be discontinued. Do not resume THALOMID treatment after angioedema and anaphylaxis [see Dosage and Administration (2.4)].

6 ADVERSE REACTIONS

The following clinically significant adverse reactions are described in detail in other labeling sections:

- Teratogenicity [see Boxed Warning, Warnings and Precautions (5.1, 5.2), and Patient Counseling Information (17)]
- Venous and Arterial Thromboembolism [see Boxed Warning, Warnings and Precautions (5.3), and Patient Counseling Information (17)]
- Increased Mortality in Patients with MM When Pembrolizumab Is Added to a Thalidomide Analogue and Dexamethasone [see Warnings and Precautions (5.4)]
- Drowsiness and Somnolence [see Warnings and Precautions (5.5)]
- Peripheral Neuropathy [see Warnings and Precautions (5.6)]
- Dizziness and Orthostatic Hypotension [see Warnings and Precautions (5.7)]
- Neutropenia [see Warnings and Precautions (5.8)]
- Thrombocytopenia [see Warnings and Precautions (5.9)]
- Increased HIV Viral Load [see Warnings and Precautions (5.10)]
- Bradycardia [see Warnings and Precautions (5.11)]
- Severe Cutaneous Reactions [see Warnings and Precautions (5.12)]
- Seizures [see Warnings and Precautions (5.13)]
- Tumor Lysis Syndrome [see Warnings and Precautions (5.14)]
- Hypersensitivity [see Warnings and Precautions (5.16)]

6.1 Clinical Trials Experience

Because clinical trials are conducted under widely varying conditions, adverse reaction rates observed in the clinical trials of a drug cannot be directly compared to rates in the clinical trials of another drug and may not reflect the rates observed in practice.

Most patients taking THALOMID can be expected to experience adverse reactions.

Adverse Reactions in Multiple Myeloma Controlled Clinical Trials

The safety analyses were conducted in two controlled clinical studies (Study 1 and Study 2). The safety analysis in Study 1 was conducted on 204 patients who received treatment. Table 1 lists the most common adverse reactions (≥ 10%). The most frequently reported adverse reactions were fatigue, hypocalcemia, edema, constipation, sensory neuropathy, dyspnea, muscle weakness, leukopenia, neutropenia, rash/desquamation, confusion, anorexia, nausea, anxiety/agitation, tremor, fever, weight loss, thrombosis/embolism, neuropathy-motor, weight gain, dizziness, and dry skin.

Twenty-three percent of patients (47/204) discontinued due to adverse reactions; 30% (31/102) from the THALOMID/dexamethasone arm and 16% (16/102) from the dexamethasone alone arm.

Table 1: Adverse Reactions Reported in ≥10% of Patients in the THALOMID/Dexamethasone Arm (Study 1 - Safety Population; N=204)
Body System Adverse Reaction | Thal + Dex* (N=102) |  | Dex Alone* (N=102)
 | All Grades n (%) | Grade 3/4 n (%) | All Grades n (%) | Grade 3/4 n (%)
Metabolic/Laboratory | 97 (95) | 33 (32) | 96 (94) | 30 (29)
Hypocalcemia | 73 (72) | 11 (11) | 60 (59) | 5 (5)
Neurology | 92 (90) | 30 (29) | 76 (74) | 18 (18)
Neuropathy-sensory | 55 (54) | 4 (4) | 28 (28) | 1 (1)
Confusion | 29 (28) | 9 (9) | 12 (12) | 3 (3)
Anxiety/agitation | 26 (26) | 1 (1) | 14 (14) | 3 (3)
Tremor | 26 (26) | 1 (1) | 6 (6) | 0 (0)
Neuropathy-motor | 22 (22) | 8 (8) | 16 (16) | 5 (5)
Dizziness/ lightheadedness | 20 (20) | 1 (1) | 14 (14) | 0 (0)
Depressed level of consciousness | 16 (16) | 3 (3) | 3 (3) | 3 (3)
Constitutional Symptoms | 91 (89) | 19 (19) | 84 (82) | 16 (16)
Fatigue | 81 (79) | 17 (17) | 72 (71) | 13 (13)
Fever | 24 (24) | 1 (1) | 20 (20) | 3 (3)
Weight loss | 23 (23) | 1 (1) | 21 (21) | 2 (2)
Weight gain | 22 (22) | 1 (1) | 13 (13) | 0 (0)
Blood/Bone Marrow | 88 (86) | 29 (29) | 96 (94) | 19 (19)
Leukocytes (decreased) | 36 (35) | 6 (6) | 30 (29) | 3 (3)
Neutrophils (decreased) | 32 (31) | 10 (10) | 24 (24) | 10 (10)
Gastrointestinal | 83 (81) | 22 (22) | 70 (69) | 8 (8)
Constipation | 56 (55) | 8 (8) | 29 (28) | 1 (1)
Anorexia | 29 (28) | 4 (4) | 25 (24) | 2 (2)
Nausea | 29 (28) | 5 (5) | 23 (22) | 1 (1)
Mouth dryness | 12 (12) | 1 (1) | 6 (6) | 0 (0)
Cardiovascular | 70 (69) | 37 (36) | 60 (59) | 21 (21)
Edema | 58 (56) | 6 (6) | 47 (46) | 4 (4)
Thrombosis/embolism | 23 (22) | 21 (21) | 5 (5) | 5 (5)
Pain | 64 (63) | 10 (10) | 66 (65) | 15 (15)
Myalgia | 17 (17) | 0 (0) | 14 (14) | 1 (1)
Arthralgia | 13 (13) | 0 (0) | 10 (10) | 2 (2)
Pulmonary | 52 (51) | 19 (19) | 51 (50) | 20 (20)
Dyspnea | 43 (42) | 13 (13) | 32 (31) | 15 (15)
Dermatology/Skin | 48 (47) | 5 (5) | 35 (34) | 2 (2)
Rash/desquamation | 31 (30) | 4 (4) | 18 (18) | 2 (2)
Dry skin | 21 (21) | 0 (0) | 11 (11) | 0 (0)
Hepatic | 47 (46) | 7 (7) | 45 (44) | 4 (4)
Bilirubin | 14 (14) | 2 (2) | 10 (10) | 2 (2)
Musculoskeletal | 42 (41) | 9 (9) | 41 (40) | 14 (14)
Muscle weakness | 41 (40) | 6 (6) | 38 (37) | 13 (13)
* Treatment-emergent adverse reactions reported in ≥10% of patients in THALOMID/dexamethasone arm and with a ≥1% difference in the THALOMID/dexamethasone arm compared to the dexamethasone alone arm.

The safety analysis in Study 2 was conducted on 466 patients who received treatment. Table 2 lists the most common adverse reactions (≥10%) that were observed. Table 3 lists the most common Grade 3/4 adverse reactions (occurring at >2%) that were observed. The adverse reactions most often reported by patients treated with THALOMID/dexamethasone were constipation, peripheral edema, tremor, asthenia, dizziness and fatigue. Adverse reactions with a frequency at least 2-fold higher in the THALOMID/dexamethasone group than in the placebo/dexamethasone group include constipation, tremor, deep vein thrombosis and peripheral sensory neuropathy.

Twenty-six percent of patients (121/466) discontinued due to adverse reactions; 37% (86/234) from the THALOMID/dexamethasone arm and 15% (35/232) from the placebo/dexamethasone arm.

Table 2: Adverse Reactions Reported in ≥10% of Patients in the THALOMID/Dexamethasone Arm (Study 2 - Safety Population; N=466)
Body System Adverse Reaction | Thal/Dex (N=234)* n (%) | Placebo/Dex (N=232)* n (%)
Patients with at least 1 Adverse Reaction | 233 (99) | 230 (99)
General Disorders and Administration Site Conditions | 176 (75) | 149 (64)
Edema peripheral | 80 (34) | 57 (25)
Asthenia | 56 (24) | 47 (20)
Fatigue | 50 (21) | 36 (16)
Edema NOS | 31 (13) | 19 (8)
Gastrointestinal Disorders | 162 (69) | 149 (64)
Constipation | 116 (50) | 49 (21)
Nausea | 30 (13) | 27 (12)
Dyspepsia | 27 (11) | 21 (9)
Nervous System Disorders | 161 (69) | 138 (60)
Tremor | 62 (26) | 29 (12)
Dizziness | 51 (23) | 32 (14)
Paresthesia | 27 (12) | 15 (6)
Peripheral sensory neuropathy | 24 (10) | 12 (5)
Infections and Infestations | 139 (59) | 138 (60)
Pneumonia NOS | 35 (15) | 28 (12)
Psychiatric Disorders | 90 (38) | 97 (42)
Anxiety | 27 (12) | 22 (10)
Depression | 24 (10) | 19 (8)
Metabolism and Nutrition Disorders | 96 (41) | 89 (38)
Hyperglycemia NOS | 36 (15) | 32 (14)
Vascular Disorders | 92 (39) | 53 (23)
Deep vein thrombosis | 30 (13) | 4 (2)
*All adverse reactions reported in ≥10% of patients in THALOMID/dexamethasone arm and with a ≥1% difference in proportion of patients between the THALOMID/dexamethasone arm compared to the placebo/dexamethasone arm.
NOS = not otherwise specified.

Table 3: Grade 3/4 Adverse Reactions Reported in >2% of Patients in the THALOMID/Dexamethasone Arm (Study 2 - Safety Population; N=466)
Body System Adverse Reaction | THALOMID/Dex (N=234)* n (%) | Placebo/Dex (N=232)* n (%)
Infections and Infestations | 50 (21) | 36 (16)
Pneumonia NOS | 17 (7) | 14 (6)
Bronchopneumonia NOS | 7 (3) | 3 (1)
General Disorders and Administration Site Conditions | 44 (19) | 26 (11)
Asthenia | 11 (5) | 4 (2)
Metabolism and Nutrition Disorders | 33 (14) | 34 (15)
Hypokalemia | 7 (3) | 3 (1)
Nervous System Disorders | 47 (20) | 20 (9)
Syncope | 8 (3) | 1 (<1)
Peripheral neuropathy NOS | 8 (3) | 0 (0)
Cerebrovascular accident | 6 (3) | 1 (<1)
Cardiac Disorders | 35 (15) | 27 (11)
Atrial fibrillation | 11 (5) | 8 (3)
Myocardial ischemia | 6 (3) | 2 (1)
Vascular Disorders | 42 (18) | 14 (6)
Deep vein thrombosis | 27 (12) | 4 (2)
Gastrointestinal Disorders | 26 (11) | 22 (10)
Constipation | 7 (3) | 2 (1)
Investigations | 21 (9) | 21 (9)
Weight increased | 8 (3) | 4 (2)
Blood and Lymphatic System Disorders | 24 (10) | 17 (7)
Neutropenia | 8 (3) | 6 (3)
Respiratory, Thoracic, and Mediastinal Disorders | 27 (12) | 13 (6)
Pulmonary embolism | 16 (7) | 4 (2)
Psychiatric Disorders | 19 (8) | 8 (3)
Anxiety | 5 (2) | 3 (1)
Confusional state | 5 (2) | 2 (1)
Ear and Labyrinth Disorders | 6 (3) | 0 (0)
Vertigo | 5 (2) | 0 (0)
* All Grade 3/4 adverse reactions with >2% of patients in THALOMID/dexamethasone arm and with a higher frequency in the THALOMID/dexamethasone arm compared to the placebo/dexamethasone arm.
NOS = not otherwise specified.

Less Common Adverse Reactions in Multiple Myeloma Controlled Clinical Trials

In Study 2, THALOMID in combination with dexamethasone in patients with multiple myeloma, the following adverse reactions not described above were reported*:

Gastrointestinal disorders: Vomiting NOS, dry mouth, peritonitis, diverticular perforation

Nervous system disorders: Somnolence, hypoesthesia, polyneuropathy NOS, transient ischemic attack

Respiratory, thoracic, and mediastinal disorders: Bronchitis NOS

Psychiatric disorders: Mood alteration NOS

Vascular disorders: Hypotension NOS, orthostatic hypotension

Cardiac disorders: Bradycardia NOS

Eye disorders: Blurred vision

* All adverse reactions with ≥3% of patients in THALOMID/dexamethasone arm and with a ≥1% difference in proportion of patients between the THALOMID/dexamethasone arm compared to the placebo/dexamethasone arm. All grade 3/4 and serious adverse reactions reported >2 patients in THALOMID/dexamethasone arm and with a percentage higher in the THALOMID/dexamethasone arm compared to the placebo/dexamethasone arm have been considered for possible inclusion. In any cases medical judgment has been applied for consideration of causality assessment.

Adverse Reactions in Erythema Nodosum Leprosum (ENL) Clinical Trials

Table 4 lists treatment-emergent signs and symptoms that occurred in THALOMID-treated patients in clinical trials in ENL. The most common adverse reactions (≥10%) reported in patients with ENL were somnolence, rash, headache. Doses ranged from 50 to 300 mg/day. All adverse reactions were mild to moderate in severity, and none resulted in discontinuation.

Table 4: Summary of Adverse Reactions (ARs) Reported in Controlled Clinical Trials
 | All ARs Reported in Patients with ENL | ARs Reported in ≥3 HIV-seropositive Patients
Body System/ Adverse Reaction | THALOMID 50 to 300 mg/day (N=24) n (%) | THALOMID 100 mg/day (N=36) n (%) | THALOMID 200 mg/day (N=32) n (%) | Placebo (N=35) n (%)
Blood and Lymphatic | 0 | 8 (22) | 13 (41) | 10 (29)
Anemia | 0 | 2 (6) | 4 (13) | 3 (9)
Leukopenia | 0 | 6 (17) | 8 (25) | 3 (9)
Lymphadenopathy | 0 | 2 (6) | 4 (13) | 3 (9)
Body as a Whole | 16 (67) | 18 (50) | 19 (59) | 13 (37)
Abdominal pain | 1 (4) | 1 (3) | 1 (3) | 4 (11)
Accidental injury | 1 (4) | 2 (6) | 0 | 1 (3)
Asthenia | 2 (8) | 2 (6) | 7 (22) | 1 (3)
Back pain | 1 (4) | 2 (6) | 0 | 0
Chills | 1 (4) | 0 | 3 (9) | 4 (11)
Facial edema | 1 (4) | 0 | 0 | 0
Fever | 0 | 7 (19) | 7 (22) | 6 (17)
Headache | 3 (13) | 6 (17) | 6 (19) | 4 (11)
Infection | 0 | 3 (8) | 2 (6) | 1 (3)
Malaise | 2 (8) | 0 | 0 | 0
Neck pain | 1 (4) | 0 | 0 | 0
Neck rigidity | 1 (4) | 0 | 0 | 0
Pain | 2 (8) | 0 | 1 (3) | 2 (6)
Digestive System | 5 (21) | 16 (44) | 16 (50) | 15 (43)
Anorexia | 0 | 1 (3) | 3 (9) | 2 (6)
Constipation | 1 (4) | 1 (3) | 3 (9) | 0
Diarrhea | 1 (4) | 4 (11) | 6 (19) | 6 (17)
Dry mouth | 0 | 3 (8) | 3 (9) | 2 (6)
Flatulence | 0 | 3 (8) | 0 | 2 (6)
Liver function tests multiple abnormalities | 0 | 0 | 3 (9) | 0
Nausea | 1 (4) | 0 | 4 (13) | 1 (3)
Oral moniliasis | 1 (4) | 4 (11) | 2 (6) | 0
Tooth pain | 1 (4) | 0 | 0 | 0
Metabolic and Endocrine Disorders | 1 (4) | 8 (22) | 12 (38) | 8 (23)
Edema peripheral | 1 (4) | 3 (8) | 1 (3) | 0
Hyperlipidemia | 0 | 2 (6) | 3 (9) | 1 (3)
SGOT increased | 0 | 1 (3) | 4 (13) | 2 (6)
Nervous System | 13 (54) | 19 (53) | 18 (56) | 12 (34)
Agitation | 0 | 0 | 3 (9) | 0
Dizziness | 1 (4) | 7 (19) | 6 (19) | 0
Insomnia | 0 | 0 | 3 (9) | 2 (6)
Nervousness | 0 | 1 (3) | 3 (9) | 0
Neuropathy | 0 | 3 (8) | 0 | 0
Paresthesia | 0 | 2 (6) | 5 (16) | 4 (11)
Somnolence | 9 (38) | 13 (36) | 12 (38) | 4 (11)
Tremor | 1 (4) | 0 | 0 | 0
Vertigo | 2 (8) | 0 | 0 | 0
Respiratory System | 3 (13) | 9 (25) | 6 (19) | 9 (26)
Pharyngitis | 1 (4) | 3 (8) | 2 (6) | 2 (6)
Rhinitis | 1 (4) | 0 | 0 | 4 (11)
Sinusitis | 1 (4) | 3 (8) | 1 (3) | 2 (6)
Skin and Appendages | 10 (42) | 17 (47) | 18 (56) | 19 (54)
Acne | 0 | 4 (11) | 1 (3) | 0
Dermatitis fungal | 1 (4) | 2 (6) | 3 (9) | 0
Nail disorder | 1 (4) | 0 | 1 (3) | 0
Pruritus | 2 (8) | 1 (3) | 2 (6) | 2 (6)
Rash | 5 (21) | 9 (25) | 8 (25) | 11 (31)
Rash maculopapular | 1 (4) | 6 (17) | 6 (19) | 2 (6)
Sweating | 0 | 0 | 4 (13) | 4 (11)
Urogenital System | 2 (8) | 6 (17) | 2 (6) | 4 (11)
Albuminuria | 0 | 3 (8) | 1 (3) | 2 (6)
Hematuria | 0 | 4 (11) | 0 | 1 (3)
Impotence | 2 (8) | 1 (3) | 0 | 0

Other Adverse Reactions Observed in ENL Patients

THALOMID in doses up to 400 mg/day has been administered investigationally in the United States over a 19-year period in 1465 patients with ENL. The published literature describes the treatment of an additional 1678 patients. To provide a meaningful estimate of the proportion of the individuals having adverse reactions, similar types of events were grouped into a smaller number of standardized categories using a modified COSTART dictionary/terminology. These categories are used in the listing below. All reported events are included except those already listed in the previous table. Due to the fact that these data were collected from uncontrolled studies, the incidence rate cannot be determined. No causal relationship between THALOMID and these events can be conclusively determined at this time. These are reports of all adverse events noted by investigators in patients to whom they had administered THALOMID.

Blood and Lymphatic: ESR decrease, eosinophilia, granulocytopenia, hypochromic anemia, leukemia, leukocytosis, leukopenia, MCV elevated, RBC abnormal, spleen palpable, thrombocytopenia.

Body as a Whole: Abdomen enlarged, fever, photosensitivity, upper extremity pain.

Cardiovascular System: Bradycardia, hypertension, hypotension, peripheral vascular disorder, tachycardia, vasodilation.

Digestive System: Anorexia, appetite increase/weight gain, dry mouth, dyspepsia, enlarged liver, eructation, flatulence, increased liver function tests, intestinal obstruction, vomiting.

Metabolic and Endocrine: ADH inappropriate, amyloidosis, bilirubinemia, BUN increased, creatinine increased, cyanosis, diabetes, edema, electrolyte abnormalities, hyperglycemia, hyperkalemia, hyperuricemia, hypocalcemia, hypoproteinemia, LDH increased, phosphorus decreased, SGPT increased.

Muscular Skeletal: Arthritis, bone tenderness, hypertonia, joint disorder, leg cramps, myalgia, myasthenia, periosteal disorder.

Nervous System: Abnormal thinking, agitation, amnesia, anxiety, causalgia, circumoral paresthesia, confusion, depression, euphoria, hyperesthesia, insomnia, nervousness, neuralgia, neuritis, neuropathy, paresthesia, peripheral neuritis, psychosis.

Respiratory System: Cough, emphysema, epistaxis, pulmonary embolus, rales, upper respiratory infection, voice alteration.

Skin and Appendages: Acne, alopecia, dry skin, eczematous rash, exfoliative dermatitis, ichthyosis, perifollicular thickening, skin necrosis, seborrhea, sweating, urticaria, vesiculobullous rash.

Special Senses: Amblyopia, deafness, dry eye, eye pain, tinnitus.

Urogenital: Decreased creatinine clearance, hematuria, orchitis, proteinuria, pyuria, urinary frequency.

Other Adverse Reactions Observed in HIV-seropositive Patients

In addition to controlled clinical trials, THALOMID has been used in uncontrolled studies in 145 patients. Less frequent adverse reactions that have been reported in these HIV-seropositive patients treated with THALOMID were grouped into a smaller number of standardized categories using modified COSTART dictionary/terminology and these categories are used in the listing below. Adverse reactions that have already been included in the tables and narrative above, or that are too general to be informative are not listed.

Blood and Lymphatic: Aplastic anemia, macrocytic anemia, megaloblastic anemia, microcytic anemia.

Body as a Whole: Ascites, AIDS, allergic reaction, cellulitis, chest pain, chills and fever, cyst, decreased CD4 count, facial edema, flu syndrome, hernia, thyroid hormone level altered, moniliasis, photosensitivity reaction, sarcoma, sepsis, viral infection.

Cardiovascular System: Angina pectoris, arrhythmia, atrial fibrillation, bradycardia, cerebral ischemia, cerebrovascular accident, congestive heart failure, deep thrombophlebitis, heart arrest, heart failure, hypertension, hypotension, murmur, myocardial infarct, palpitation, pericarditis, peripheral vascular disorder, postural hypotension, syncope, tachycardia, thrombophlebitis, thrombosis.

Digestive System: Cholangitis, cholestatic jaundice, colitis, dyspepsia, dysphagia, esophagitis, gastroenteritis, gastrointestinal disorder, gastrointestinal hemorrhage, gum disorder, hepatitis, pancreatitis, parotid gland enlargement, periodontitis, stomatitis, tongue discoloration, tooth disorder.

Metabolic and Endocrine: Avitaminosis, bilirubinemia, dehydration, hypercholesterolemia, hypoglycemia, increased alkaline phosphatase, increased lipase, increased serum creatinine, peripheral edema.

Muscular Skeletal: Myalgia, myasthenia.

Nervous System: Abnormal gait, ataxia, decreased libido, decreased reflexes, dementia, dysesthesia, dyskinesia, emotional lability, hostility, hypalgesia, hyperkinesia, incoordination, meningitis, neurologic disorder, tremor, vertigo.

Respiratory System: Apnea, bronchitis, lung disorder, lung edema, pneumonia (including Pneumocystis carinii pneumonia), rhinitis.

Skin and Appendages: Angioedema, benign skin neoplasm, eczema, herpes simplex, incomplete Stevens-Johnson syndrome, nail disorder, pruritus, psoriasis, skin discoloration, skin disorder.

Special Senses: Conjunctivitis, eye disorder, lacrimation disorder, retinitis, taste perversion.

6.2 Postmarketing Experience

The following additional adverse reactions have been identified during post approval use of THALOMID and are not already included in Clinical Trials Experience [see Adverse Reactions (6.1)]. Because these reactions are reported voluntarily from a population of uncertain size, it is not always possible to reliably estimate their frequency or establish a causal relationship to drug exposure.

Blood and Lymphatic: Decreased white blood cell counts including febrile neutropenia, changes in prothrombin time, pancytopenia, chronic myelogenous leukemia, nodular sclerosing Hodgkin's disease, erythroleukemia, lymphedema, lymphopenia.

Body as a Whole: Hangover effect

Cardiovascular System: Sick sinus syndrome, EKG abnormalities, pulmonary hypertension.

Digestive System: Intestinal perforation, gastrointestinal perforations, bile duct obstruction, stomach ulcer, aphthous, stomatitis.

Ear and Labyrinthine Disorders: Hearing impairment.

Immune System Disorders: Hypersensitivity including anaphylaxis, solid organ transplant rejection.

Infections and infestations: Severe infections (e.g., fatal sepsis including septic shock), viral infections (including varicella zoster virus, cytomegalovirus, and hepatitis B virus reactivation) and progressive multifocal leukoencephalopathy (PML).

Metabolic and Endocrine: Electrolyte imbalance including hypercalcemia, hyponatremia and hypomagnesemia, hypothyroidism, increased alkaline phosphatase, tumor lysis syndrome, myxedema.

Nervous System: Changes in mental status or mood including suicide attempts, disturbances in consciousness including lethargy, loss of consciousness or stupor, seizures including grand mal convulsions and status epilepticus, Parkinson's disease, stroke, carpal tunnel, Raynaud's syndrome, migraine, foot drop.

Renal and Urinary Disorders: Renal failure, acute renal failure, oliguria, enuresis.

Reproductive System and Breast Disorders: amenorrhea, sexual dysfunction, galactorrhea, gynecomastia, metrorrhagia.

Respiratory System: Pleural effusion, interstitial lung disease.

Skin and Appendages: Erythema multiforme, erythema nodosum, toxic epidermal necrolysis (TEN), drug reaction with eosinophilia and systemic symptoms (DRESS), purpura, petechiae.

Special Senses: Diplopia, nystagmus

7 DRUG INTERACTIONS

7.1 Opioids, Antihistamines, Antipsychotics, Anti-anxiety Agents, or Other CNS Depressants (Including Alcohol)

The use of opioids, antihistamines, antipsychotics, anti-anxiety agents, or other CNS depressants concomitantly with THALOMID may cause an additive sedative effect and should be avoided.

7.2 Drugs which Cause Bradycardia

The use of drugs which slow cardiac conduction concomitantly with THALOMID may cause an additive bradycardic effect and should be used with caution. Cardiovascular medications which may cause bradycardia include calcium channel blockers, beta blockers, alpha/beta-adrenergic blockers, and digoxin. Non-cardiac drugs that may cause bradycardia include H2 blockers (e.g., famotidine, cimetidine), lithium, tricyclic antidepressants and neuromuscular blockers (succinylcholine).

In 16 healthy men, the pharmacokinetic profile of a single 0.5 mg digoxin dose was similar with and without the coadministration of THALOMID 200 mg/day at steady state levels. The single dose of digoxin had no effect on the pharmacokinetic profile of THALOMID. The safety of long-term concomitant use of THALOMID and digoxin has not been evaluated.

7.3 Drugs which Cause Peripheral Neuropathy

The use of drugs which cause peripheral neuropathy (e.g., bortezomib, amiodarone, cisplatin, docetaxel, paclitaxel, vincristine, disulfiram, phenytoin, metronidazole, alcohol) can cause an additive effect and should be used with caution.

7.4 Hormonal Contraceptives

Hormonal contraceptives increase the risk of thromboembolism. It is not known whether concomitant use of hormonal contraceptives further increases the risk of thromboembolism with THALOMID.

In 10 healthy women, the pharmacokinetic profiles of norethindrone and ethinyl estradiol following administration of a single dose containing 1.0 mg of norethindrone acetate and 75 mcg of ethinyl estradiol were studied. The results were similar with and without coadministration of THALOMID 200 mg/day to steady-state levels.

7.5 Warfarin

In 13 healthy men, the pharmacokinetic profile and international normalized ratio (INR) of prothrombin time for warfarin, following a single oral dose of 25 mg, were similar with and without the coadministration of THALOMID 200 mg/day at steady-state levels. The single dose of warfarin had no effect on the pharmacokinetic profile of thalidomide.

7.6 Drugs that Interfere with Hormonal Contraceptives

Concomitant use of HIV-protease inhibitors, griseofulvin, modafinil, penicillins, rifampin, rifabutin, phenytoin, carbamazepine, or certain herbal supplements such as St. John's Wort with hormonal contraceptive agents may reduce the effectiveness of the contraception up to one month after discontinuation of these concomitant therapies. Therefore, females requiring treatment with one or more of these drugs must use two OTHER effective or highly effective methods of contraception while taking THALOMID.

7.7 Concomitant Therapies that may Increase the Risk of Thromboembolism

Erythropoietic agents, or other agents that may increase the risk of thromboembolism, such as estrogen containing therapies, should be used with caution in multiple myeloma patients receiving THALOMID with dexamethasone [see Warnings and Precautions (5.3)].

8 USE IN SPECIFIC POPULATIONS

8.1 Pregnancy

Pregnancy Exposure Registry

There is a pregnancy exposure registry that monitors pregnancy outcomes in females exposed to THALOMID during pregnancy as well as female partners of male patients who are exposed to THALOMID. This registry is also used to understand the root cause for the pregnancy. Report any suspected fetal exposure to THALOMID to the FDA via the MedWatch program at 1-800-FDA-1088 and to the REMS Call Center at 1-888-423-5436.

Risk Summary

Based on the mechanism of action [see Clinical Pharmacology (12.1)], human and animal data (see Data), THALOMID can cause embryo-fetal harm when administered to a pregnant female and is contraindicated during pregnancy [see Boxed Warning, Contraindications (4.1), and Warnings and Precautions (5.1)].

THALOMID is a human teratogen, inducing a high frequency of severe and life-threatening birth defects such as amelia (absence of limbs), phocomelia (short limbs), hypoplasticity of the bones, absence of bones, external ear abnormalities (including anotia, micropinna, small or absent external auditory canals), facial palsy, eye abnormalities (anophthalmos, microphthalmos), and congenital heart defects. Alimentary tract, urinary tract, and genital malformations have also been documented and mortality at or shortly after birth has been reported in about 40% of infants. Even a single dose taken by a pregnant woman can cause birth defects. If this drug is used during pregnancy, or if the patient becomes pregnant while taking this drug, the patient should be apprised of the potential risk to a fetus.

If pregnancy does occur during treatment, immediately discontinue the drug. Under these conditions, refer the patient to an obstetrician/gynecologist experienced in reproductive toxicity for further evaluation and counseling. Report any suspected fetal exposure to THALOMID to the FDA via the MedWatch program at 1-800-FDA-1088 and also the REMS Call Center at 1-888-423-5436.

Thalidomide crossed the placenta after administration to pregnant hamsters (see Data).

The estimated background risk of major birth defects and miscarriage for the indicated population is unknown. All pregnancies have a background risk of birth defect, loss, or other adverse outcomes. The estimated background risk in the U.S. general population of major birth defects is 2%-4% and of miscarriage is 15%-20% of clinically recognized pregnancies.

Data

Animal Data

A pre- and postnatal reproductive toxicity study was conducted in pregnant female rabbits. Compound-related increased abortion incidences and elevated fetotoxicity were observed at the lowest oral dose level of 30 mg/kg/day (approximately 1.5-fold the maximum human dose based upon BSA) and all higher dose levels. Neonatal mortality was elevated at oral dose levels to the lactating female rabbits ≥150 mg/kg/day (approximately 7.5-fold the maximum human dose based upon BSA). No delay in postnatal development, including learning and memory functions, were noted at the oral dose level to the lactating female rabbits of 150 mg/kg/day (average thalidomide concentrations in milk ranged from 22 to 36 mcg per mL).

In a study conducted in pregnant rabbits, thalidomide levels in fetal plasma were approximately 11% to 73% of the maternal Cmax. In a study conducted with ^14C-thalidomide (150 mg/kg orally) in pregnant hamsters, radioactivity was detected in the embryo, and the relative concentrations of radioactivity in the embryo and maternal plasma were about the same at 4, 12 and 24 hours after dosing. Based on the radioactivity data, thalidomide crossed the placental barrier, and the fetal levels of drug-related material were approximately similar to those of maternal levels.

8.2 Lactation

Risk Summary

There is no information regarding the presence of thalidomide in human milk, the effects of THALOMID on the breastfed child, or the effects of THALOMID on milk production. Thalidomide is excreted in the milk of lactating rabbits (see Data). Because many drugs are excreted in human milk and because of the potential for adverse reactions in a breastfed child from THALOMID, advise women not to breastfeed during treatment with THALOMID.

Data

Animal Data

In lactating female rabbits at an oral dose of 150 mg/kg/day, the average thalidomide concentrations in milk ranged from 22 to 36 mcg per mL. In the study of lactating female rabbits, high concentrations of thalidomide (7741 – 71425 ng per mL) were noted in milk during four weeks of pre-weaning period. Milk concentrations were 1.16 - 2.11, 1.05 – 2.43, and 0.64 – 3.63 times that of plasma at 30, 150 and 500 mg/kg thalidomide doses, respectively; thalidomide, as a lipophilic compound, distributed into milk, with concentrations attained similar to or slightly higher than those of systemic concentrations.

8.3 Females and Males of Reproductive Potential

Pregnancy Testing

THALOMID can cause fetal harm when administered during pregnancy [see Use in Specific Populations (8.1)]. Verify the pregnancy status of females of reproductive potential prior to initiating THALOMID therapy and during therapy. Advise females of reproductive potential that they must avoid pregnancy 4 weeks before therapy, while taking THALOMID, during dose interruptions and for at least 4 weeks after completing therapy.

Females of reproductive potential must have 2 negative pregnancy tests before initiating THALOMID. The first test should be performed within 10-14 days, and the second test within 24 hours prior to prescribing THALOMID. Once treatment has started and during dose interruptions, pregnancy testing for females of reproductive potential should occur weekly during the first 4 weeks of use, then pregnancy testing should be repeated every 4 weeks in females with regular menstrual cycles. If menstrual cycles are irregular, the pregnancy testing should occur every 2 weeks. Pregnancy testing and counseling should be performed if a patient misses her period or if there is any abnormality in her menstrual bleeding. THALOMID treatment must be discontinued during this evaluation.

Contraception

Females

Females of reproductive potential must commit either to abstain continuously from heterosexual sexual intercourse or to use 2 methods of reliable birth control simultaneously: one highly effective form of contraception – tubal ligation, IUD, hormonal (birth control pills, injections, hormonal patches, vaginal rings, or implants), or partner's vasectomy, and 1 additional effective contraceptive method – male latex or synthetic condom, diaphragm, or cervical cap. Contraception must begin 4 weeks prior to initiating treatment with THALOMID, during therapy, during dose interruptions, and continuing for 4 weeks following discontinuation of THALOMID therapy. Reliable contraception is indicated even where there has been a history of infertility, unless due to hysterectomy. Females of reproductive potential should be referred to a qualified provider of contraceptive methods, if needed.

Males

Thalidomide is present in the semen of males who take THALOMID. Therefore, males must always use a latex or synthetic condom during any sexual contact with females of reproductive potential while taking THALOMID, during dose interruptions and for up to 28 days after discontinuing THALOMID, even if they have undergone a successful vasectomy. Male patients taking THALOMID must not donate sperm.

Infertility

Based on findings in animals, male fertility may be compromised by treatment with THALOMID [see Nonclinical Toxicology (13.1)].

8.4 Pediatric Use

Safety and effectiveness in pediatric patients below the age of 12 years have not been established.

8.5 Geriatric Use

One hundred and seventy-six (52%) of 336 patients treated with THALOMID in combination with dexamethasone were ≥65 of age while 50 (15%) were ≥75. Patients ≥65 years of age on Study 2 had higher incidences of atrial fibrillation, constipation, fatigue, nausea, hypokalemia, deep venous thrombosis, hyperglycemia, pulmonary embolism, and asthenia compared to patients <65.

9 DRUG ABUSE AND DEPENDENCE

Physical and psychological dependence has not been reported in patients taking THALOMID; however, as with other tranquilizers/hypnotics, thalidomide has been reported to result in habituation to its soporific effects.

10 OVERDOSAGE

There is no specific antidote for a THALOMID overdose. In the event of an overdose, the patient's vital signs should be monitored and appropriate supportive care given to maintain blood pressure and respiratory status.

11 DESCRIPTION

THALOMID, α-(N-phthalimido) glutarimide, is an immunomodulatory agent. The empirical formula for thalidomide is C13H10N2O4 and the gram molecular weight is 258.2. The CAS number of thalidomide is 50-35-1.

Chemical Structure of Thalidomide

Note: ∙ = asymmetric carbon atom

Thalidomide is an off-white to white, odorless, crystalline powder that is soluble at 25°C in dimethyl sulfoxide and sparingly soluble in water and ethanol. The glutarimide moiety contains a single asymmetric center and, therefore, may exist in either of two optically active forms designated S-(-) or R-(+). THALOMID is an equal mixture of the S-(-) and R-(+) forms and, therefore, has a net optical rotation of zero.

THALOMID is available in 50 mg, 100 mg, 150 mg and 200 mg capsules for oral administration. Active ingredient: thalidomide. Inactive ingredients: pregelatinized starch and magnesium stearate. The 50 mg capsule shell contains gelatin, titanium dioxide, and black ink. The 100 mg capsule shell contains black iron oxide, yellow iron oxide, titanium dioxide, gelatin, and black ink. The 150 mg capsule shell contains FD&C blue #2, black iron oxide, yellow iron oxide, titanium dioxide, gelatin, and black and white ink. The 200 mg capsule shell contains FD&C blue #2, titanium dioxide, gelatin, and white ink.

12 CLINICAL PHARMACOLOGY

12.1 Mechanism of Action

The mechanism of action of THALOMID is not fully understood. Cellular activities of thalidomide are mediated through its target cereblon, a component of a cullin ring E3 ubiquitin ligase enzyme complex. THALOMID possesses immunomodulatory, anti-inflammatory and antiangiogenic properties. Available data from in vitro studies and clinical trials suggest that the immunologic effects of this compound can vary substantially under different conditions, but may be related to suppression of excessive tumor necrosis factor-alpha (TNF-α) production and down-modulation of selected cell surface adhesion molecules involved in leukocyte migration. For example, administration of thalidomide has been reported to decrease circulating levels of TNF-α in patients with erythema nodosum leprosum (ENL); however, it has also been shown to increase plasma TNF-α levels in HIV-seropositive patients. Other anti-inflammatory and immunomodulatory properties of thalidomide may include suppression of macrophage involvement in prostaglandin synthesis, and modulation of interleukin-10 and interleukin-12 production by peripheral blood mononuclear cells. Thalidomide treatment of multiple myeloma patients is accompanied by an increase in the number of circulating natural killer cells, and an increase in plasma levels of interleukin-2 and interferon-gamma (T cell-derived cytokines associated with cytotoxic activity). Thalidomide was found to inhibit angiogenesis in a human umbilical artery explant model in vitro. The cellular processes of angiogenesis inhibited by thalidomide may include the proliferation of endothelial cells.

12.3 Pharmacokinetics

Absorption

Absorption of THALOMID is slow after oral administration. The maximum plasma concentrations are reached approximately 2-5 hours after administration. The absolute bioavailability of thalidomide from thalidomide capsules has not yet been characterized in human subjects due to its poor aqueous solubility. Based on the ^14C-radiolabel thalidomide study in human, greater than 90% of the total radioactivity is recovered in urine suggesting good oral absorption. While the extent of absorption (as measured by area under the curve [AUC]) is proportional to dose in healthy subjects, the observed peak concentration (Cmax) increased in a less than proportional manner (see Table 5 below). This lack of Cmax dose proportionality, coupled with the observed increase in Tmax values, suggests that the poor solubility of thalidomide in aqueous media may be hindering the rate of absorption.

Table 5: Pharmacokinetic Parameter Values for THALOMID Mean (%CV)
Population/ Single Dose | AUC0-∞ mcg∙hr/mL | Cmax mcg/mL | Tmax (hrs) | Half-life (hrs)
Healthy Subjects (n=14)
50 mg | 4.9 (16%) | 0.62 (52%) | 2.9 (66%) | 5.52 (37%)
200 mg | 18.9 (17%) | 1.76 (30%) | 3.5 (57%) | 5.53 (25%)
400 mg | 36.4 (26%) | 2.82 (28%) | 4.3 (37%) | 7.29 (36%)
Patients with Hansen's Disease (n=6)
400 mg | 46.4 (44.1%) | 3.44 (52.6%) | 5.7 (27%) | 6.86 (17%)

Coadministration of THALOMID (thalidomide) with a high-fat meal causes minor (<10%) changes in the observed AUC and Cmax values; however, it causes an increase in Tmax to approximately 6 hours.

Distribution

In human plasma, the geometric mean plasma protein binding was 55% and 66%, respectively, for (+)-(R)- and (-)-(S)-thalidomide. In a pharmacokinetic study of thalidomide in HIV-seropositive adult male subjects receiving thalidomide 100 mg/day, thalidomide was detectable in the semen.

Metabolism

In a ^14C-radiolabel ADME study in humans, unchanged drug is the predominant circulating component. Thalidomide is not a substrate of the cytochrome P450 system. At therapeutic concentrations, thalidomide is not an inhibitor or inducer of human cytochrome P450 enzymes in vitro. Pharmacokinetic drug-drug interactions with substrates, inhibitors or inducers of CYP450 are not anticipated.

Elimination

The mean elimination half-life of thalidomide in plasma following single oral doses between 50 mg and 400 mg was 5.5 to 7.3 hours. Following a single 400 mg oral dose of radiolabeled thalidomide, the total mean recovery was 93.6% of the administered dose by Day 8. The majority of the radioactive dose was excreted within 48 hours following dose administration. In humans, ^14C-thalidomide is primarily excreted in urine (91.9% of the radioactive dose) mainly as hydrolytic metabolites while fecal excretion is minor (<2% of the dose). Unchanged thalidomide is not eliminated by the kidney to a notable degree (<3.5% of the dose).

Effects of Weight

There is a linear relationship between body weight and estimated thalidomide clearance. In MM patients with body weight from 47-133 kg, thalidomide clearance ranged from approximately 6-12 L/h, representing an increase in thalidomide clearance of 0.605 L/h per 10 kg body weight increase.

Effects of Age, Gender and Race

Analysis of the data from pharmacokinetic studies in healthy volunteers and patients with Hansen's disease ranging in age from 20 to 69 years does not reveal any age-related changes.

While a comparative trial of the effects of gender on thalidomide pharmacokinetics has not been conducted, examination of the data for thalidomide does not reveal any significant gender differences in pharmacokinetic parameter values.

Pharmacokinetic differences due to race have not been studied.

Pharmacokinetic Data in Special Populations

HIV-seropositive Subjects: There is no apparent significant difference in measured pharmacokinetic parameter values between healthy human subjects and HIV-seropositive subjects following single-dose administration of THALOMID Capsules.

Patients with Hansen's Disease: Analysis of data from a small study in Hansen's patients suggests that these patients, relative to healthy subjects, may have an increased bioavailability of THALOMID. The increase is reflected both in an increased area under the curve and in increased peak plasma levels. The clinical significance of this increase is unknown.

Pediatric: No pharmacokinetic data are available in subjects below the age of 18 years.

Patients with Renal Impairment: Renal impairment is not expected to influence drug exposure since <3.5% of the dose is excreted in the urine as unchanged drug.

Patients with Hepatic Impairment: No clinical studies have been conducted in patients with hepatic impairment.

13 NONCLINICAL TOXICOLOGY

13.1 Carcinogenesis, Mutagenesis, Impairment of Fertility

Two-year carcinogenicity studies were conducted in male and female rats and mice. No compound-related tumorigenic effects were observed at the highest dose levels of 3,000 mg/kg/day to male and female mice (38-fold greater than the highest recommended daily human dose of 400 mg based upon body surface area [BSA]), 3,000 mg/kg/day to female rats (75-fold the maximum human dose based upon BSA), and 300 mg/kg/day to male rats (7.5-fold the maximum human dose based upon BSA).

Thalidomide was neither mutagenic nor genotoxic in the following assays: the Ames bacterial (S. typhimurium and E. coli) reverse mutation assay, a Chinese hamster ovary cell (AS52/XPRT) forward mutation assay, and an in vivo mouse micronucleus test.

Fertility studies were conducted in male and female rabbits; no compound-related effects in mating and fertility indices were observed at any oral thalidomide dose level including the highest of 100 mg/kg/day to female rabbits and 500 mg/kg/day to male rabbits (approximately 5- and 25- fold the maximum human dose, respectively, based upon BSA). Testicular pathological and histopathological effects (classified as slight) were seen in male rabbits at dose levels ≥30 mg/kg/day (approximately 1.5-fold the maximum human dose based upon BSA).

14 CLINICAL STUDIES

14.1 Multiple Myeloma (MM)

The efficacy and safety of THALOMID in patients with multiple myeloma were evaluated in two randomized, multi-center studies (Study 1 and Study 2). Study 1 was an open-label study which randomized 207 symptomatic patients with newly diagnosed MM to THALOMID plus dexamethasone (N = 103) versus dexamethasone alone (N=104). The THALOMID dose was 200 mg daily and the dexamethasone dose was 40 mg orally once daily on days 1-4, 9-12, and 17-20 every 28-days. Each group was treated for four 28-day cycles.

Study 2 randomized 470 newly diagnosed patients with MM to THALOMID plus dexamethasone (N=235) versus placebo plus dexamethasone (N=235). In the THALOMID/dexamethasone arm, a starting dose of thalidomide 50 mg was escalated to 200 mg/day (cycle 2) once daily for 28 days. Patients in both treatment groups took 40 mg of dexamethasone once daily given on days 1-4, 9-12, and 17-20 (every 28 days). Beginning with Cycle 5, the dose of dexamethasone was reduced to 40 mg once daily on Days 1 to 4 of each cycle. Treatment continued as tolerated until disease progression.

Baseline demographics for both studies are presented in Table 6 and disease characteristics for the study population are summarized in Tables 7 (Study 1) and 8 (Study 2).

Table 6: Baseline Patient Demographics
Characteristic | Study 1 |  | Study 2
Characteristic | THALOMID/ Dexamethasone (N=103) | Dexamethasone (N=104) | THALOMID/ Dexamethasone (N=235) | Placebo/ Dexamethasone (N=235)
Age (years)
Median | 65 | 68 | 65 | 66
Range | 37 - 83 | 38 - 83 | 39 - 86 | 31 - 84
Gender^1, N (%)
Male | 53 (51) | 61 (59) | 118 (50) | 120 (51)
Female | 50 (49) | 42 (40) | 117 (50) | 115 (49)
Race^2, N (%)
Caucasian | 90 (87) | 90 (87) | 224 (95) | 221 (94)
Black | 11 (11) | 11 (11) | 7 (3) | 10 (4)
Other | 1 (1) | 2 (2) | 4 (2)^3 | 4 (2)^4
^1 Missing information in Study 1 for 1 patient in the Dex alone group
^2 Missing information in Study 1 for 1 patient per arm
^3 Black/Hispanic [1 (0.4%)], Hispanic [2 (0.9%)], Hispanic/White [1 (0.4%)], Other [0 (0.0%)]
^4 Hispanic [1 (0.4%)], Asian/Pacific Islander [2 (0.9%)], Other [1 (0.4%)]

Table 7: Baseline Disease Characteristics (Study 1)
Disease Characteristic | THALOMID/Dexamethasone (N=103) | Dexamethasone alone (N=104)
Stage (Durie-Salmon), N (%)^1
I | 14 (13.6%) | 17 (16.3%)
II | 47 (45.6%) | 44 (42.3%)
III | 41 (39.8%) | 43 (41.3%)
Immunoglobulin Type, N (%)^2
IgA | 21 (20.4%) | 22 (21.2%)
IgG | 63 (61.2%) | 60 (57.7%)
IgM | 0 (0.0%) | 1 (1.0%)
Biclonal | 0 (0.0%) | 1 (1.0%)
Lytic Lesions^3
None | 28 (27.1%) | 14 (13.5%)
1-3 lesions | 24 (23.3%) | 19 (18.3%)
>3 lesions | 34 (33.0%) | 41 (39.4%)
Serum Light Chain^4
Kappa | 59 (57.3%) | 53 (51.0%)
Lambda | 28 (27.2%) | 40 (38.5%)
^1 Missing information for 1 patient in Thal + Dex arm
^2 Missing information for 19 patients in Thal + Dex arm and 20 patients in Dex alone arm
^3 Missing information for 17 patients in Thal + Dex arm and 30 patients in Dex alone arm
^4 Missing information for 16 patients in Thal + Dex arm and 11 patients in Dex alone arm

Table 8: Baseline Disease Characteristics (Study 2)
Disease Characteristic | THALOMID/Dexamethasone (N=235) | Placebo/Dexamethasone (N=235)
Baseline MM Stage (Durie-Salmon), n (%)
I | 2 (1) | 2 (1)
II | 76 (32) | 88 (37)
III | 157 (69) | 145 (62)
ECOG Performance Status, n (%)
0 | 40 (17) | 54 (23)
1 | 124 (53) | 112 (48)
2 | 70 (30) | 68 (29)
3 | 0 (0) | 1 (<1)
Missing | 1 (<1) | 0 (0)
Lytic Bone Lesions, n (%)
Present | 185 (79) | 188 (80)
Absent | 49 (21) | 46 (20)
Missing | 1 (<1) | 1 (<1)
Bone Marrow Aspirate/Biopsy Cellularity, n (%)
Normal | 102 (43) | 108 (46)
Hyperplasia | 77 (33) | 76 (32)
Hypoplasia | 53 (23) | 50 (21)
Missing | 3 (1) | 1 (<1)
Baseline β-2 Microglobulin, n (%)
≤2.5 mg/L | 33 (14) | 35 (15)
>2.5 mg/L | 200 (85) | 199 (85)
Missing | 2 (1) | 1 (<1)
KEY: ECOG=Eastern Cooperative Oncology Group

In Study 1, response rate was the primary endpoint. Response rates based on serum or urine paraprotein measurements were significantly higher in the combination arm (52% vs. 36%). The primary efficacy endpoint in Study 2 was time to progression (TTP), defined as the time from randomization to the first documentation of disease progression, based on the myeloma response criteria. A preplanned interim analysis for Study 2 demonstrated that the combination of THALOMID plus dexamethasone was superior to placebo plus dexamethasone with respect to TTP (Table 9).

Table 9: Summary of Efficacy (Study 2)
 | Thalidomide/Dexamethasone (N=235) | Placebo/Dexamethasone (N=235)
Time to Progression
Progressed – n (%) | 72 (31) | 126 (54)
Median (Weeks) (95% CIa) | 97.7 (61.86, NR) | 28.3 (27.71, 36.43)
Hazard Ratio (95% CI)b | 0.43 (0.32, 0.58)
P-valuec | < 0.0001
Overall Survival
Death – n (%) | 57 (24) | 68 (29)
Median (Weeks) (95% CIa) | NR (112.14, NR) | 128.6 (113.43, NR)
Hazard Ratio (95% CI)b | 0.82 (0.57, 1.16)
Myeloma Response Rated – n (%)
Complete Response (CR) | 18 (8) | 6 (3)
Partial Response (PR) | 130 (55) | 102 (43)
Overall Response (CR + PR) | 148 (63) | 108 (46)
95% CI (%) | (56, 69) | (39, 53)
a The 95% confidence intervals about the median overall TTP, or median overall survival. CI: confidence interval; NR: not reached.
b Based on a proportional hazards model comparing the hazard functions associated with treatment groups (thalidomide/dexamethasone:placebo/dexamethasone).
c P-value based on the interim analysis was compared with the nominal significance level of 0.0027. Based on a one-sided unstratified log rank test of survival curve differences between treatment groups.
d Disease response assessments were determined according to the Bladé criteria. Response is the highest assessment of response during the treatment phase of the study.

The Kaplan-Meier plot of the time to progression by treatment group is presented in Figure 1.

Figure 1: Kaplan-Meier Plot of Time to Disease Progression

KEY: Placebo/Dex=placebo/dexamethasone; Thal/Dex=THALOMID/dexamethasone

14.2 Erythema Nodosum Leprosum (ENL)

The primary data demonstrating the efficacy of thalidomide in the treatment of the cutaneous manifestations of moderate to severe ENL are derived from the published medical literature and from a retrospective study of 102 patients treated by the U.S. Public Health Service.

Two double-blind, randomized, controlled trials reported the dermatologic response to a 7-day course of 100 mg thalidomide (four times daily) or control. Dosage was lower for patients under 50 kg in weight.

Table 10: Double-Blind, Controlled Clinical Trials of Thalidomide in Patients with ENL: Cutaneous Response
Reference | No. of Patients | No. Treatment Courses* | Percent Responding**
Iyer et al. Bull World Health Organization 1971;45:719 | 92 | 204 | Thalidomide 75% | Aspirin 25%
Sheskin et al. Int J Lep 1969;37:135 | 52 | 173 | Thalidomide 66% | Placebo 10%
* In patients with cutaneous lesions
**Iyer: Complete response or lesions absent
**Sheskin: Complete improvement + "striking" improvement (i.e., >50% improvement)

Waters reported the results of two studies, both double-blind, randomized, placebo-controlled, crossover trials in a total of 10 hospitalized, steroid-dependent patients with chronic ENL treated with 100 mg thalidomide or placebo (three times daily). All patients also received dapsone. The primary endpoint was reduction in weekly steroid dosage.

Table 11: Double-Blind, Controlled Trial of Thalidomide in Patients with ENL: Reduction in Steroid Dosage
Reference | Duration of Treatment | No. of Patients | Number Responding
Reference | Duration of Treatment | No. of Patients | Thalidomide | Placebo
Waters | 4 weeks | 9 | 4/5 | 0/4
Lep Rev 1971;42:26 | 6 weeks (crossover) | 8 | 8/8 | 1/8

Data on the efficacy of thalidomide in prevention of ENL relapse were derived from a retrospective evaluation of 102 patients treated under the auspices of the U.S. Public Health Service. A subset of patients with ENL controlled on thalidomide demonstrated repeated relapse upon drug withdrawal and remission with reinstitution of therapy.

Twenty U.S. patients between the ages of 11 and 17 years were treated with thalidomide, generally at 100 mg daily. Response rates and safety profiles were similar to that observed in the adult population.

Thirty-two other published studies containing over 1600 patients consistently report generally successful treatment of the cutaneous manifestations of moderate to severe ENL with thalidomide.

15 REFERENCES

1. OSHA Hazardous Drugs. OSHA [Accessed on 02 July 2014, from http://www.osha.gov/SLTC/hazardousdrugs/index.html].

16 HOW SUPPLIED/STORAGE AND HANDLING

(THIS PRODUCT IS ONLY SUPPLIED TO PHARMACIES CERTIFIED IN THE THALOMID REMS PROGRAM - See BOXED WARNING)

16.1 How Supplied

50 mg capsules [white opaque], imprinted "BMS/50 mg" with a "Do Not Get Pregnant" logo.
Individual blister packs of 1 capsule (NDC 59572-205-17).
Individual blister packs of 28 capsules (NDC 59572-205-14).

100 mg capsules [tan], imprinted "BMS/100 mg" with a "Do Not Get Pregnant" logo.
Individual blister packs of 28 capsules (NDC 59572-210-15).

150 mg capsules [tan and blue], imprinted "BMS/150 mg" with a "Do Not Get Pregnant" logo.
Individual blister packs of 28 capsules (NDC 59572-215-13).

200 mg capsules [blue], imprinted "BMS/200 mg" with a "Do Not Get Pregnant" logo.
Individual blister packs of 28 capsules (NDC 59572-220-16).

16.2 Storage

This drug must not be repackaged.

Store at 20°C- 25°C (68°F -77°F); excursions permitted to 15-30º C (59-86º F). [See USP Controlled Room Temperature]. Protect from light.

16.3 Handling and Disposal

Care should be exercised in handling of THALOMID. THALOMID capsules should not be opened or crushed. If powder from THALOMID contacts the skin, wash the skin immediately and thoroughly with soap and water. If THALOMID contacts the mucous membranes, flush thoroughly with water.

Procedures for proper handling and disposal of anticancer drugs should be considered. Several guidelines on the subject have been published^1.

Rx only and only able to be prescribed and dispensed under the terms of the THALOMID REMS Restricted Distribution Program.

17 PATIENT COUNSELING INFORMATION

Advise the patient to read the FDA-approved Patient Labeling (Medication Guide)

Embryo-Fetal Toxicity

Advise patients that THALOMID is contraindicated in pregnancy and can cause serious birth defects or death to a developing baby [see Boxed Warning, Contraindications (4.1), Warnings and Precautions (5.1), and Use in Specific Populations (8.1)].

- Advise females of reproductive potential that they must avoid pregnancy while taking THALOMID and for at least 4 weeks after completing therapy.
- Initiate THALOMID treatment in females of reproductive potential only following a negative pregnancy test.
- Advise females of reproductive potential of the importance of monthly pregnancy tests and the need to use 2 different forms of contraception, including at least 1 highly effective form, simultaneously during THALOMID therapy, during therapy interruption and for 4 weeks after she has completely finished taking THALOMID. Highly effective forms of contraception other than tubal ligation include IUD and hormonal (birth control pills, injections, patch or implants) and a partner's vasectomy. Additional effective contraceptive methods include latex or synthetic condom, diaphragm and cervical cap.
- Instruct patient to immediately stop taking THALOMID and contact her healthcare provider if she becomes pregnant while taking this drug, if she misses her menstrual period, or experiences unusual menstrual bleeding, if she stops taking birth control, or if she thinks FOR ANY REASON that she may be pregnant.
- Advise patient that if her healthcare provider is not available, she should call the REMS Call Center at 1-888-423-5436 [see Warnings and Precautions (5.1) and Use in Specific Populations (8.1)].
- Advise males to always use a latex or synthetic condom during any sexual contact with females of reproductive potential while taking THALOMID and for up to 4 weeks after discontinuing THALOMID, even if they have undergone a successful vasectomy.
- Advise male patients taking THALOMID that they must not donate sperm [see Warnings and Precautions (5.1) and Use in Specific Populations (8.3)].
- All patients must be instructed to not donate blood while taking THALOMID and for 4 weeks following discontinuation of THALOMID [see Warnings and Precautions (5.1)].

THALOMID REMS Program

Because of the risk of embryo-fetal toxicity, THALOMID is only available through a restricted program called the THALOMID REMS program [see Warnings and Precautions (5.2)].

- Patients must sign a Patient-Physician Agreement Form and comply with the requirements to receive THALOMID. In particular, females of reproductive potential must comply with the pregnancy testing, contraception requirements and participate in monthly telephone surveys. Males must comply with the contraception requirements [see Use in Specific Populations (8.3)].
- THALOMID is available only from pharmacies that are certified in THALOMID REMS program. Provide patients with the telephone number and website for information on how to obtain the product.

Pregnancy Exposure Registry

Inform females there is a Pregnancy Exposure Registry that monitors pregnancy outcomes in females exposed to THALOMID during pregnancy and that they can contact the Pregnancy Exposure Registry by calling 1-888-423-5436 [see Use in Specific Populations (8.1)].

Venous and Arterial Thromboembolism

Inform patients of the potential risk of developing venous thromboembolism (such as DVT and PE), ischemic heart disease (including myocardial infarction), and stroke, and discuss the need for appropriate prophylactic treatment [see Boxed Warning and Warnings and Precautions (5.3)].

Drowsiness and Somnolence

Inform patients of the risk of drowsiness and somnolence with the drug and to avoid situations where drowsiness or somnolence may be a problem and not to take other medications that may cause drowsiness or somnolence without adequate medical advice [see Warnings and Precautions (5.5)].

Peripheral Neuropathy

Inform patients of the risk of peripheral neuropathy and report the signs and symptoms associated with this event to their health care provider for further evaluation [see Warnings and Precautions (5.6)].

Dizziness and Orthostatic Hypotension

Inform patients of the risk of dizziness and orthostatic hypotension with the drug. Inform patients to sit upright for a few minutes prior to standing [see Warnings and Precautions (5.7)].

Neutropenia

Inform patients on the risk of developing neutropenia and the need to monitor their white blood cell count [see Warnings and Precautions (5.8)].

Thrombocytopenia

Inform patients of the risk of developing thrombocytopenia and the need to monitor their platelet count [see Warnings and Precautions (5.9)].

Increased HIV Viral Load

Inform HIV seropositive patients of the risk of increased viral load and the need to monitor viral load [see Warnings and Precautions (5.10)].

Bradycardia

Inform patients of the risk of bradycardia and report signs and symptoms associated with this event to their healthcare provider for evaluation [see Warnings and Precautions (5.11)].

Severe Cutaneous Reactions

Inform patients of the potential risk for severe skin reactions such as SJS, TEN and DRESS and report any signs and symptoms associated with these events to their healthcare provider for evaluation [see Warnings and Precautions (5.12)].

Seizures

Inform patients of the risk of seizures and report any seizure while taking THALOMID [see Warnings and Precautions (5.13)].

Tumor Lysis Syndrome

Inform patients of the potential risk of tumor lysis syndrome and report any signs and symptoms associated with this event to their healthcare provider for evaluation [see Warnings and Precautions (5.14)].

Contraceptive Risks

Inform patients that some contraceptive methods may pose a higher risk of adverse effects or may be medically contraindicated in some patients treated with THALOMID [see Warnings and Precautions (5.15), Drug Interactions (7.4, 7.7)].

Hypersensitivity

Inform patients of the potential for severe hypersensitivity reactions such as angioedema and anaphylaxis to THALOMID. Instruct patients to contact their healthcare provider right away for signs of a skin reaction. Advise patients to seek emergency medical attention for signs or symptoms of severe hypersensitivity reactions [see Warnings and Precautions (5.16)].

Marketed by:
Bristol-Myers Squibb Company
Princeton, NJ 08543 USA

THALOMID® and THALOMID REMS® are trademarks of Celgene Corporation, a Bristol-Myers Squibb company.

THALPLYPI.029/MG.027

MEDICATION GUIDE
THALOMID® (tha-lo-mid)
(thalidomide)
capsules

What is the most important information I should know about THALOMID?

Before you begin taking THALOMID, you must read and agree to all of the instructions in the THALOMID REMS® program. For more information, call 1-888-423-5436 or go to www.thalomidrems.com. Before prescribing THALOMID, your healthcare provider will explain the THALOMID REMS program to you and have you sign the Patient-Physician Agreement Form.

THALOMID can cause serious side effects including:

- Severe and life-threatening human birth defects (deformed babies) or death of an unborn baby. Females who are pregnant or who plan to become pregnant must not take THALOMID.
- Females must not get pregnant:
  - For at least 4 weeks before starting THALOMID
  - While taking THALOMID
  - During any breaks (interruptions) in your treatment with THALOMID
  - For at least 4 weeks after stopping THALOMID
- Females who can become pregnant:
  - Will have pregnancy tests weekly for 4 weeks, then every 4 weeks if your menstrual cycle is regular, or every 2 weeks if your menstrual cycle is irregular.
  - If you miss your period or have unusual bleeding, you will need to have a pregnancy test and receive counseling.
  - Must agree to use two acceptable forms of birth control at the same time, for at least 4 weeks before, while taking, during any breaks (interruptions) in your treatment, and for at least 4 weeks after stopping THALOMID.
  - Talk with your healthcare provider to find out about options for acceptable forms of birth control that you may use to prevent pregnancy before, during, and after treatment with THALOMID.
  - Stop taking THALOMID and call your healthcare provider right away if you have unprotected sex or if you think your birth control has failed.
- If you become pregnant while taking THALOMID, stop taking it right away and call your healthcare provider. If your healthcare provider is not available, you should call the REMS Call Center at 1-888-423-5436. Healthcare providers and patients should report all cases of pregnancy to:
  - FDA MedWatch at 1-800-FDA-1088, and
  - REMS Call Center at 1-888-423-5436

There is a pregnancy exposure registry that monitors the outcomes of females who take THALOMID during pregnancy, or if their male partner takes THALOMID and they are exposed during pregnancy. You can enroll in this registry by calling the REMS Call Center at the phone number listed above.

- THALOMID can pass into human semen:
  - Males, including those who have had a vasectomy, must always use a latex or synthetic condom during any sexual contact with a pregnant female or a female that can become pregnant while taking THALOMID, during any breaks (interruptions) in your treatment with THALOMID, and for up to 4 weeks after stopping THALOMID.
  - Do not have unprotected sexual contact with a female who is or could become pregnant. Tell your healthcare provider if you do have unprotected sexual contact with a female who is or could become pregnant.
  - Do not donate sperm while taking THALOMID, during any breaks (interruptions) in your treatment, and for 4 weeks after stopping THALOMID. If a female becomes pregnant with your sperm, the baby may be exposed to THALOMID and may be born with birth defects.
- Men, if your female partner becomes pregnant, you should call your healthcare provider right away.
- Blood clots. People with multiple myeloma (MM) who take THALOMID may have an increased risk for blood clots in their arteries, veins, and lungs. This risk is even higher if you take the medicine dexamethasone with THALOMID to treat your MM. Heart attacks and strokes may also happen if you take THALOMID with dexamethasone.
  Before taking THALOMID, tell your healthcare provider about all the medicines you take. Certain other medicines can also increase your risk for blood clots.
  Call your healthcare provider or get medical help right away if you get any of the following during treatment with THALOMID:
  - Signs or symptoms of a blood clot in the lung, arm, or leg may include: shortness of breath, chest pain, or arm or leg swelling
  - Signs or symptoms of a heart attack may include: chest pain that may spread to the arms, neck, jaw, back, or stomach area (abdomen), feeling sweaty, shortness of breath, feeling sick or vomiting
  - Signs or symptoms of stroke may include: sudden numbness or weakness, especially on one side of the body, severe headache or confusion, or problems with vision, speech, or balance

What is THALOMID?
THALOMID is a prescription medicine used:

- to treat people who have been newly diagnosed with multiple myeloma (MM) in combination with the medicine dexamethasone.
- to treat people who have moderate to severe new lesions of leprosy. THALOMID is not used by itself to treat the skin lesions when there is moderate to severe nerve pain.
- as maintenance treatment to prevent and keep the skin lesions of leprosy from coming back (recurring).

It is not known if THALOMID is safe and effective in children under 12 years of age.

Who should not take THALOMID?
Do not take THALOMID if you:

- are pregnant, plan to become pregnant, or become pregnant during treatment with THALOMID. See "What is the most important information I should know about THALOMID?"
- are allergic to thalidomide or any of the ingredients in THALOMID. See the end of this Medication Guide for a complete list of ingredients in THALOMID.

What should I tell my healthcare provider before taking THALOMID?
Before you take THALOMID, tell your healthcare provider about all of your medical conditions, including if you:

- have a history of seizures
- drink alcohol
- plan to have surgery
- are breastfeeding. THALOMID must not be used by females who are breastfeeding. It is not known if THALOMID passes into your breast milk and can harm your baby.

Tell your healthcare provider about all the medicines you take, including prescription and over-the-counter medicines, vitamins, and herbal supplements. THALOMID and other medicines may affect each other, causing serious side effects. Talk with your healthcare provider before taking any new medicines. Certain medicines can affect the way that birth control pills, injections, transdermal systems (patches), or implants work. You could become pregnant. See "What is the most important information I should know about THALOMID?"
Know the medicines you take. Keep a list of them to show your healthcare provider and pharmacist.

How should I take THALOMID?

- Take THALOMID exactly as prescribed and follow all the instructions of the THALOMID REMS program.
- Keep THALOMID in the blister pack until you take your daily dose.
- Swallow THALOMID capsules whole with water.
- THALOMID is taken 1 time each day, at least 1 hour after your evening meal. Bedtime is the preferred time to take THALOMID.
- Do not open or crush THALOMID capsules or handle them any more than needed.
  - If powder from the THALOMID capsule comes in contact with your skin, wash the skin right away with soap and water.
  - If powder from the THALOMID capsule comes in contact with the inside of your eyes, nose, and mouth, flush well with water.
- If you miss a dose of THALOMID and it has been less than 12 hours since your regular time, take it as soon as you remember. If it has been more than 12 hours, just skip your missed dose. Do not take 2 doses at the same time.
- If you take too much THALOMID, call your healthcare provider right away.

What should I avoid while taking THALOMID?

- See "What is the most important information I should know about THALOMID?"
- Females: Do not get pregnant and do not breastfeed while taking THALOMID.
- Males: Do not donate sperm.
- Do not share THALOMID with other people. It may cause birth defects and other serious problems.
- Do not donate blood while you take THALOMID, during any breaks (interruptions) in your treatment, and for 4 weeks after stopping THALOMID. If someone who is pregnant gets your donated blood, her baby may be exposed to THALOMID and may be born with birth defects.
- THALOMID can cause drowsiness and sleepiness. Avoid drinking alcohol, operating machinery, and driving a car when taking THALOMID. Avoid taking other medicines that may cause drowsiness without talking to your healthcare provider first.

What are the possible side effects of THALOMID?
THALOMID can cause serious side effects, including:

- See "What is the most important information I should know about THALOMID?"
- Drowsiness and sleepiness. See "What should I avoid while taking THALOMID?"
- Nerve damage. Nerve damage is common with THALOMID. If the nerve damage is severe, it may not go away. Stop taking THALOMID and call your healthcare provider right away if you have any of these early symptoms of nerve damage in your hands, legs, or feet:

- numbness

- tingling

- pain

- burning sensation

- Dizziness and decreased blood pressure when changing positions. THALOMID may cause a decrease in your blood pressure, and you may feel dizzy when you go from a lying down or sitting position to standing up. When changing positions, sit upright for a few minutes before standing to help prevent this.
- Decreased white blood cell count. THALOMID can cause decreased white blood cell counts, including neutrophils. Neutrophils are a type of white blood cell that is important in fighting bacterial infections. Your healthcare provider should check your white blood count before and regularly while you take THALOMID. If your neutrophils are too low you should not start THALOMID and if they are low during treatment, your dose of THALOMID may need to be changed.
- Decreased platelet count. THALOMID can cause decreased platelet counts. Your healthcare provider should check your platelet count before and regularly while you take THALOMID. If your platelets are too low, your healthcare provider may lower your dose, delay your dose, or completely stop treatment. Tell your healthcare provider if you have signs and symptoms of bleeding such as:

- small red or purple spots on your body
- unusual bleeding or bruising
- nosebleeds

- bright red or tar like stools
- vomiting or coughing up blood

- Increased HIV virus in the blood. If you are HIV positive, your healthcare provider should check your viral load after one month and three months of treatment, then every 3 months after that.
- Slow heartbeat (bradycardia). Tell your healthcare provider if you have a slow heartbeat, fainting, dizziness or shortness of breath.
- Severe skin reactions and severe allergic reactions. Severe skin reactions and severe allergic reactions can happen with THALOMID and may cause death.
  Call your healthcare provider right away if you develop any of the following signs or symptoms during treatment with THALOMID:

- a red, itchy, skin rash
- peeling of your skin or blisters

- severe itching
- fever

Get emergency medical help right away if you develop any of the following signs or symptoms during treatment with THALOMID:

- swelling of your lips, mouth, tongue, or throat
- trouble breathing or swallowing

- raised red areas on your skin (hives)
- a very fast heartbeat
- you feel dizzy or faint

- Seizures. Tell your healthcare provider right away if you have a seizure while taking THALOMID.
- Tumor Lysis Syndrome (TLS). TLS is caused by the fast breakdown of cancer cells. TLS can cause kidney failure and the need for dialysis treatment, abnormal heart rhythm, seizure and sometimes death. Your healthcare provider may do blood tests to check you for TLS.
- Birth control risks. Certain birth control methods may pose a higher risk of serious side effects and should not be used in some females. These risks include severe decreased white blood cell counts, low platelet counts, and blood clots. Use of an intrauterine device (IUD) or implantable birth control may also increase your risk of infection or bleeding during insertion, removal or during use of the device.

Your healthcare provider may tell you to decrease your dose, temporarily stop or permanently stop taking THALOMID if you develop certain serious side effects during treatment with THALOMID.

The most common side effects of THALOMID for treatment of multiple myeloma include:

- tiredness
- decreased calcium levels
- swelling of the hands and feet
- constipation
- numbness or tingling
- shortness of breath
- muscle weakness
- low blood counts
- skin rash or peeling. See "Severe skin reactions and severe allergic reactions" above.
- confusion
- decreased appetite

- nausea
- anxiety
- decreased energy or strength
- tremor
- fever
- weight loss
- blood clots
- muscle twitching and cramping
- weight gain
- dizziness
- dry skin

The most common side effects of THALOMID for treatment of leprosy include:

- sleepiness

- rash

- headache

These are not all the possible side effects of THALOMID.
Call your doctor for medical advice about side effects. You may report side effects to the FDA at 1-800-FDA-1088.

How should I store THALOMID?

- Store THALOMID at room temperature between 68°F to 77°F (20°C to 25°C).
- Protect from light.
- Return any unused THALOMID to THALOMID REMS by calling 1-888-423-5346 or your healthcare provider.

Keep THALOMID and all medicines out of the reach of children.

General information about the safe and effective use of THALOMID.
Medicines are sometimes prescribed for purposes other than those listed in a Medication Guide. Do not take THALOMID for conditions for which it was not prescribed. Do not give THALOMID to other people, even if they have the same symptoms you have. It may harm them and may cause birth defects. You can ask your healthcare provider or pharmacist for information about THALOMID that is written for health professionals. For more information, call 1-888-423-5436 or go to www.thalomidrems.com.

What are the ingredients in THALOMID?
Active ingredient: thalidomide
Inactive ingredients: pregelatinized starch and magnesium stearate.
The 50 mg capsule shell contains gelatin, titanium dioxide and black ink.
The 100 mg capsule shell contains black iron oxide, yellow iron oxide, titanium dioxide, gelatin, and black ink.
The 150 mg capsule shell contains FD&C blue #2, black iron oxide, yellow iron oxide, titanium dioxide, gelatin, and black and white ink.
The 200 mg capsule shell contains FD&C blue #2, titanium dioxide, gelatin, and white ink.

Marketed by: Bristol-Myers Squibb Company, Princeton, NJ 08543 USA
THALOMID® and THALOMID REMS® are trademarks of Celgene Corporation, a Bristol-Myers Squibb company.
THALPLYMG.027 3/2023

This Medication Guide has been approved by the U.S. Food and Drug Administration.
Revised: March 2023

Package Label - Principal Display Panel – 50 mg Carton

Package Label - Principal Display Panel – 100 mg Carton

Package Label - Principal Display Panel – 150 mg Carton

Package Label - Principal Display Panel – 200 mg Carton